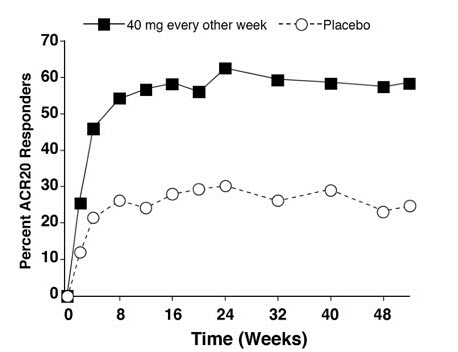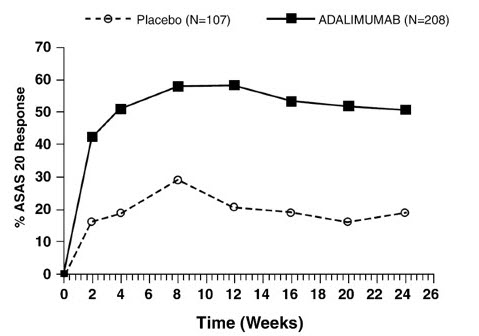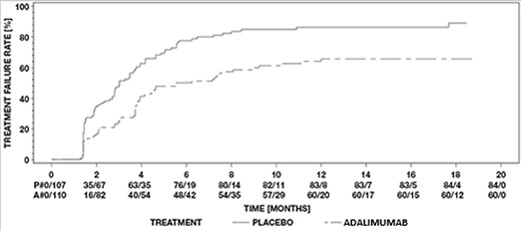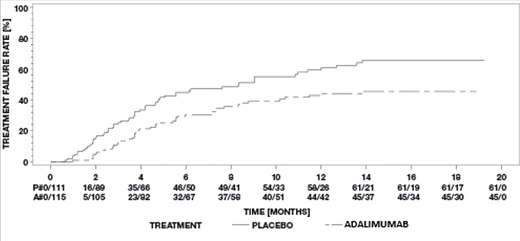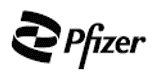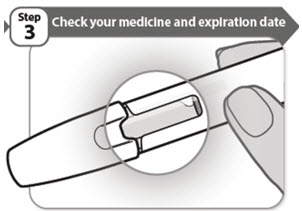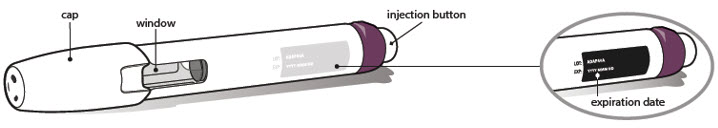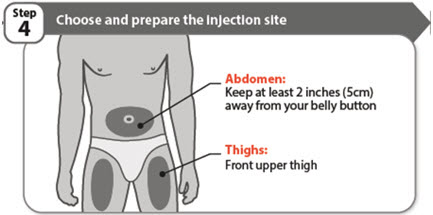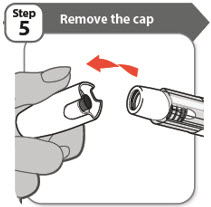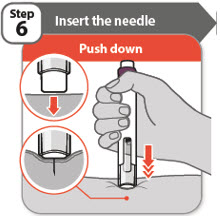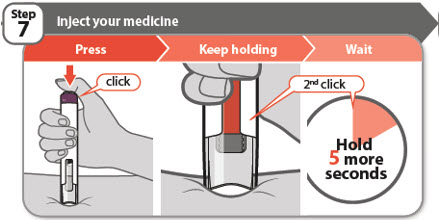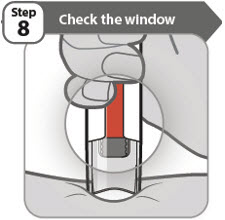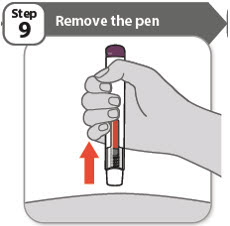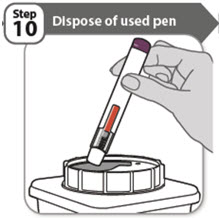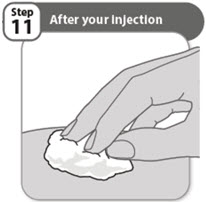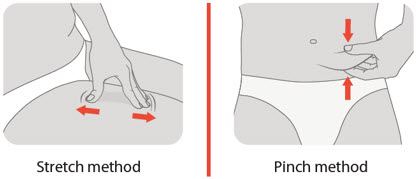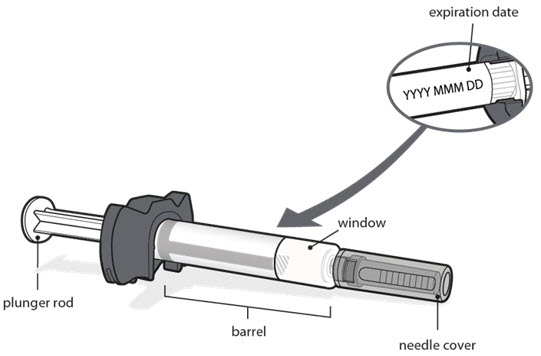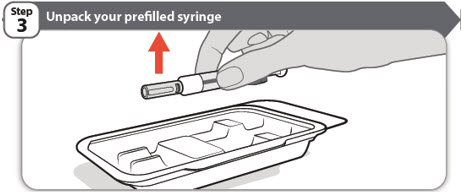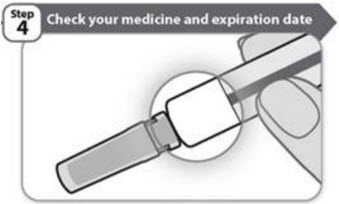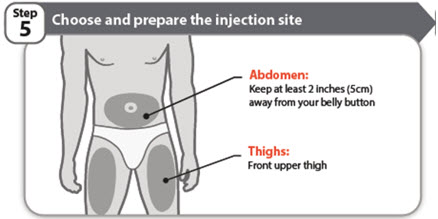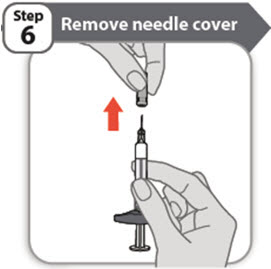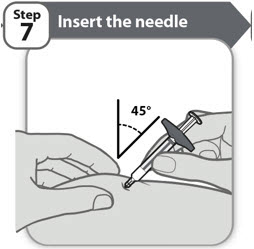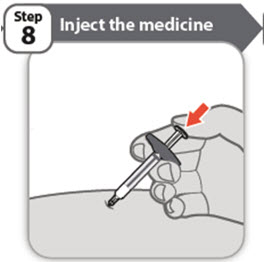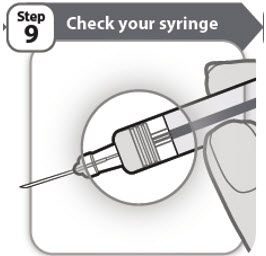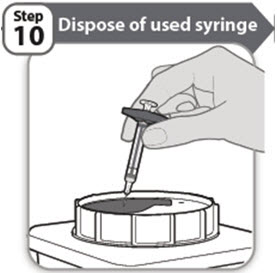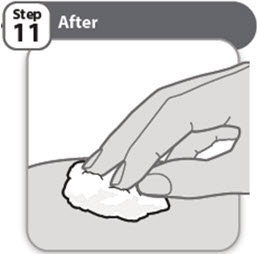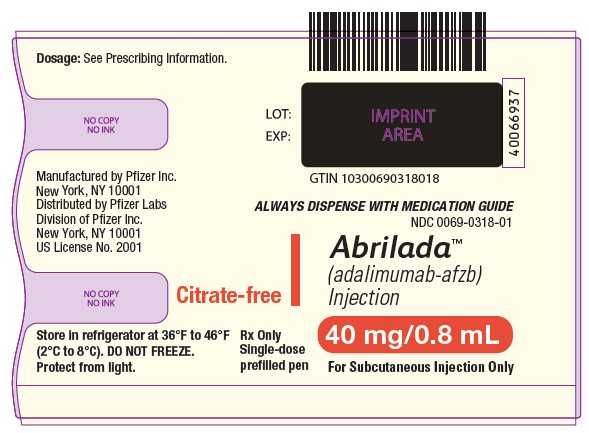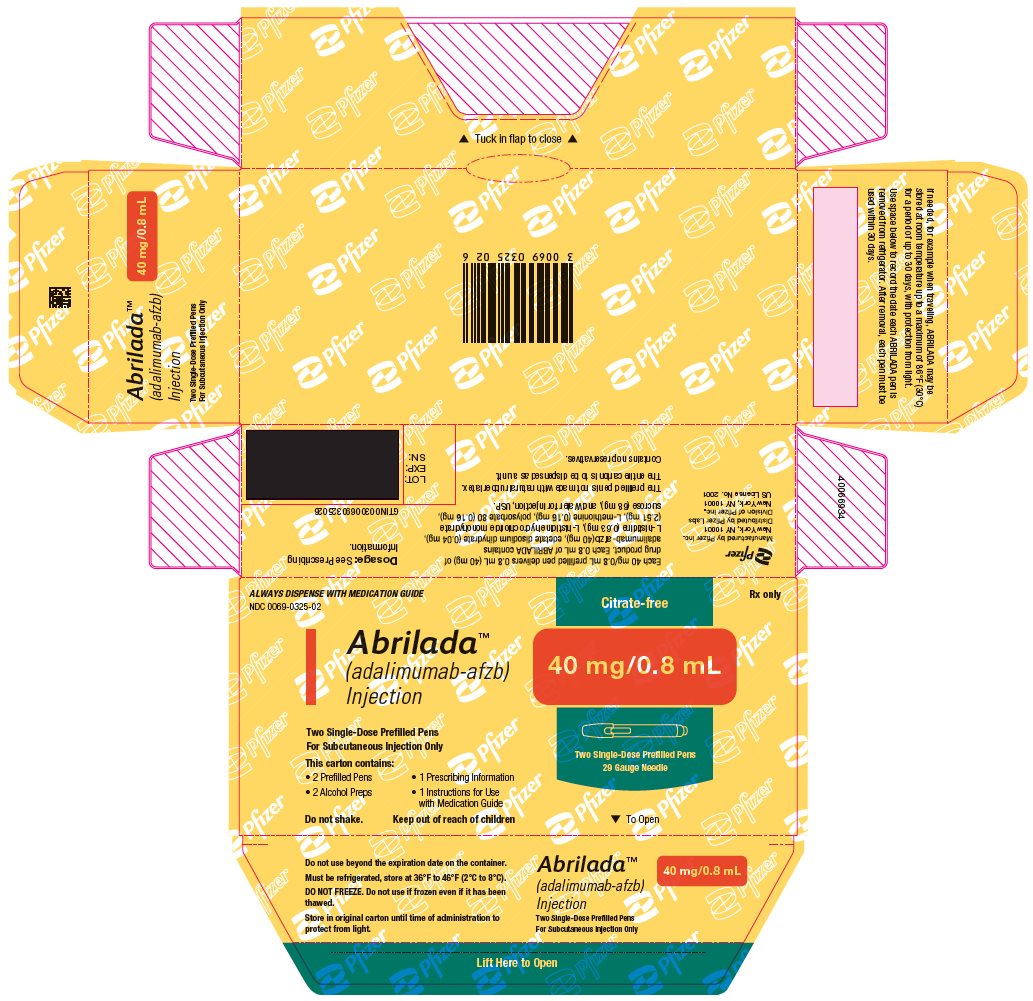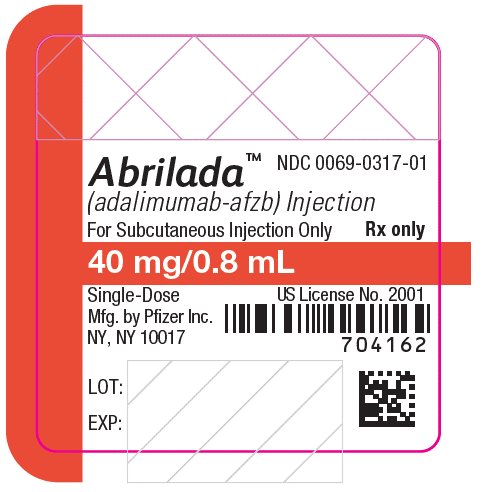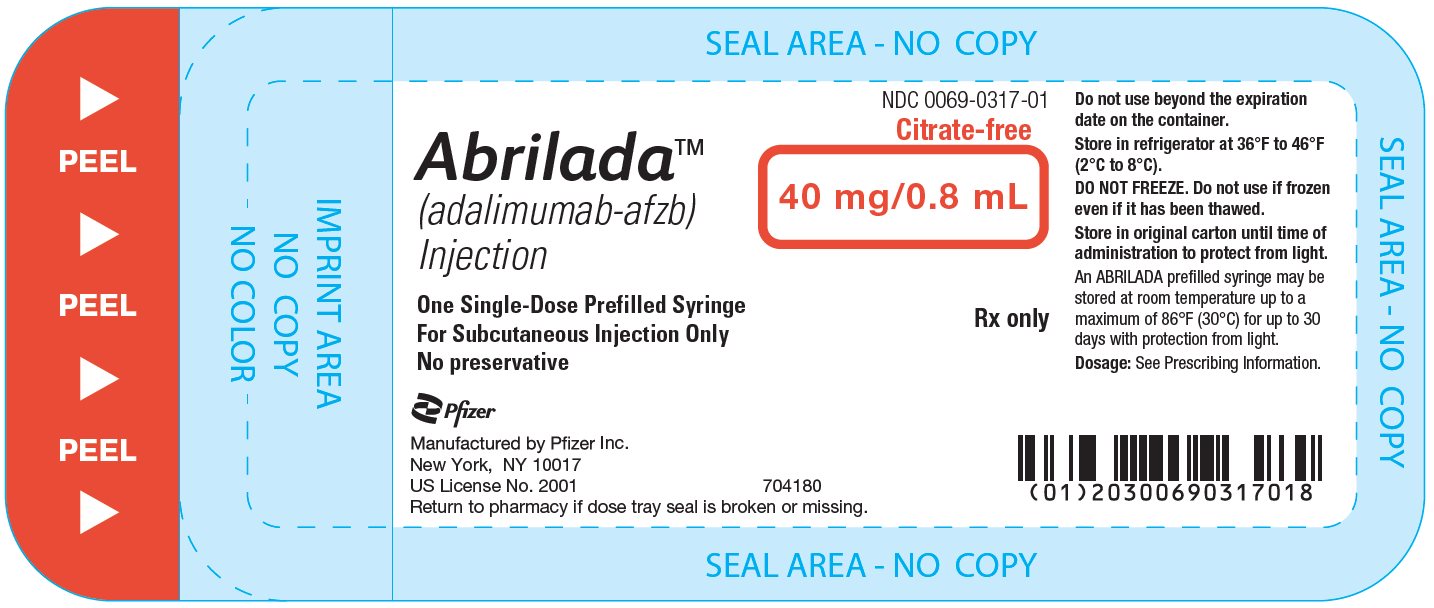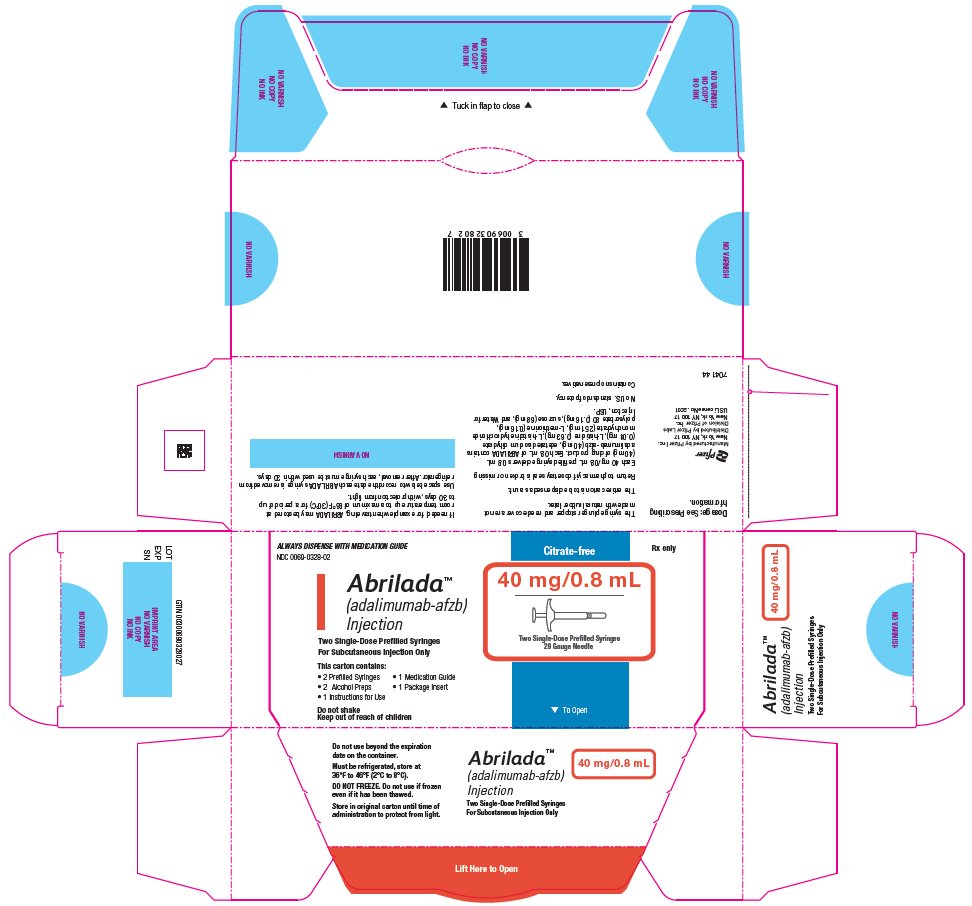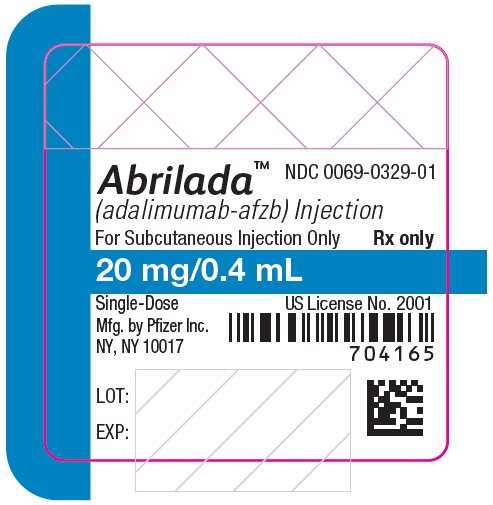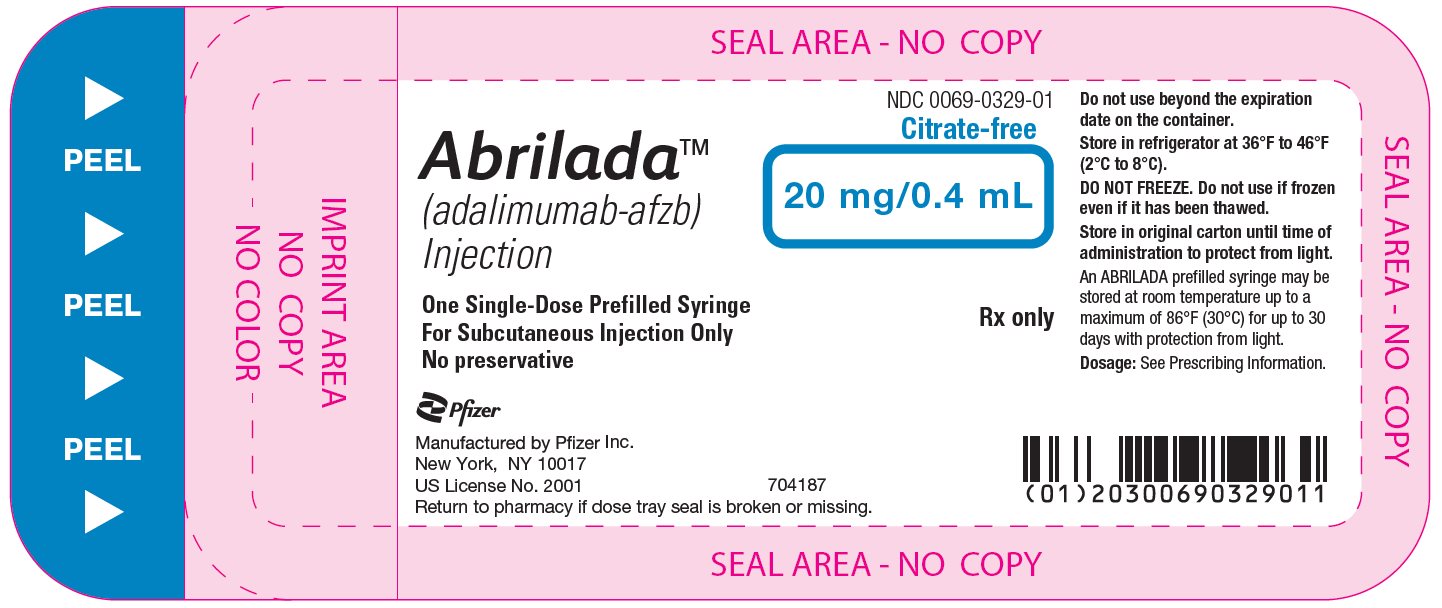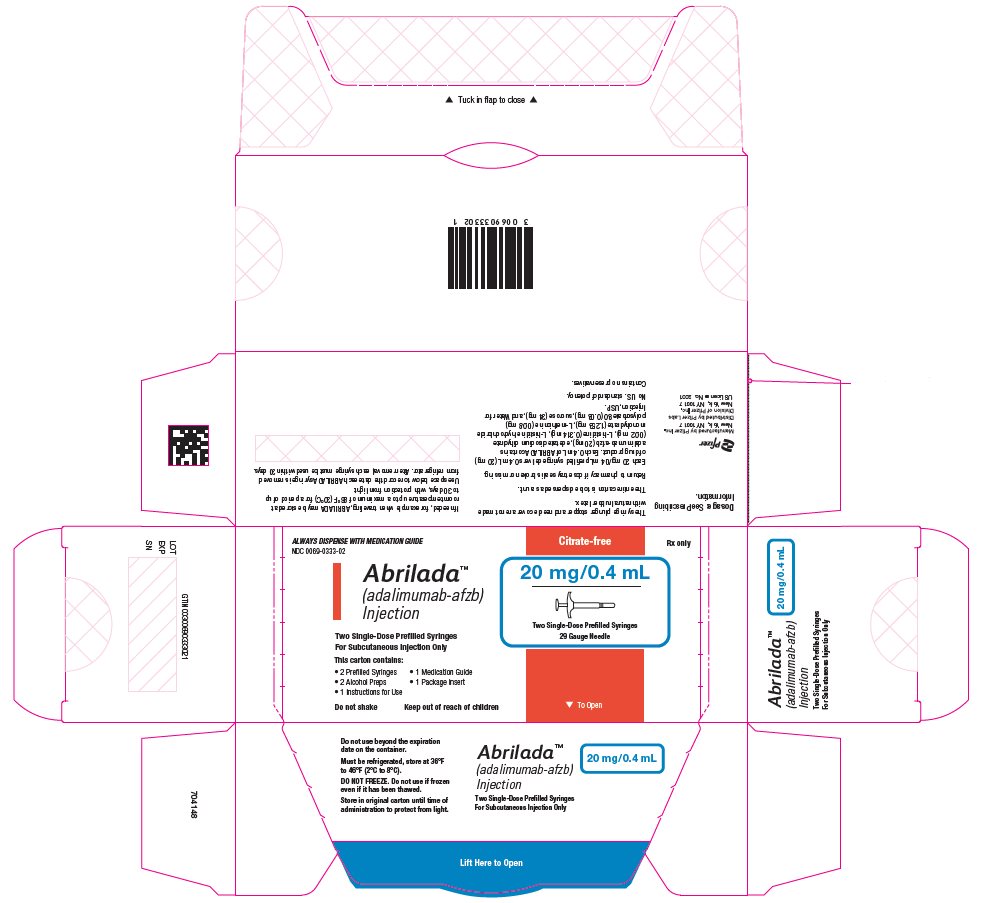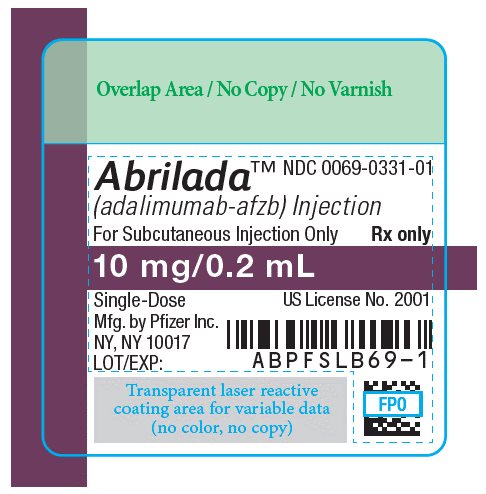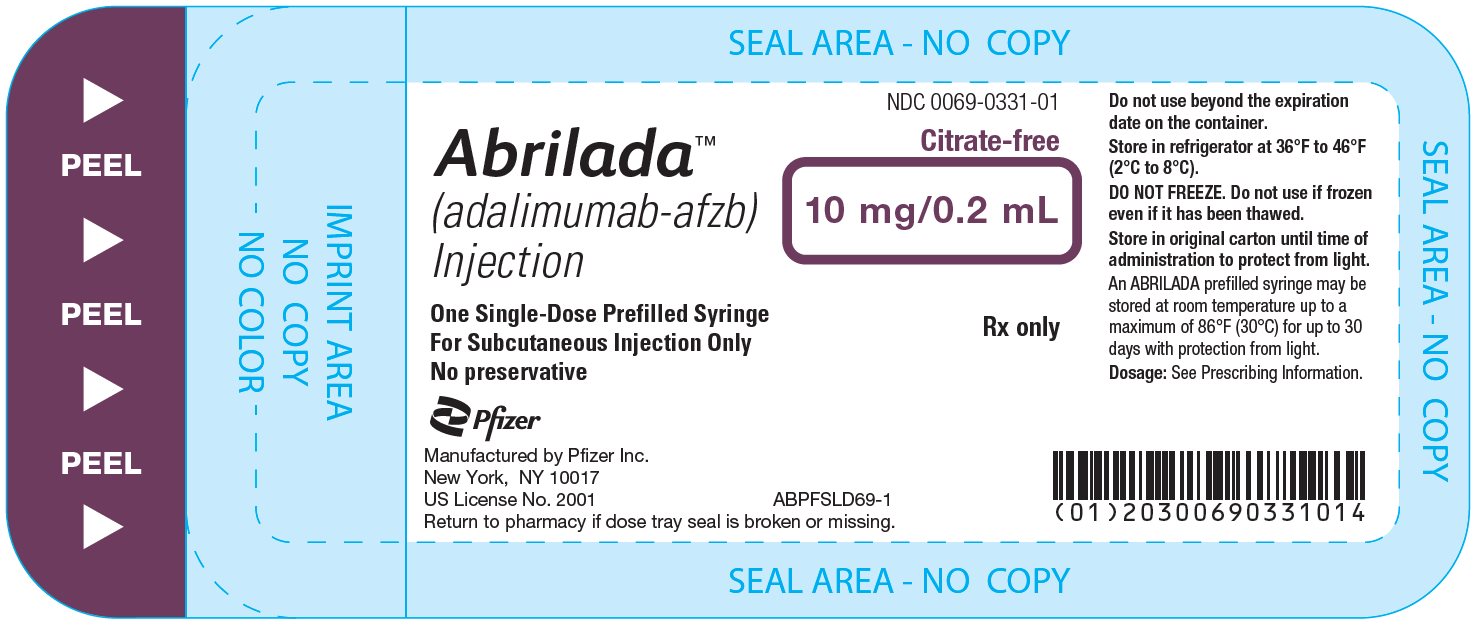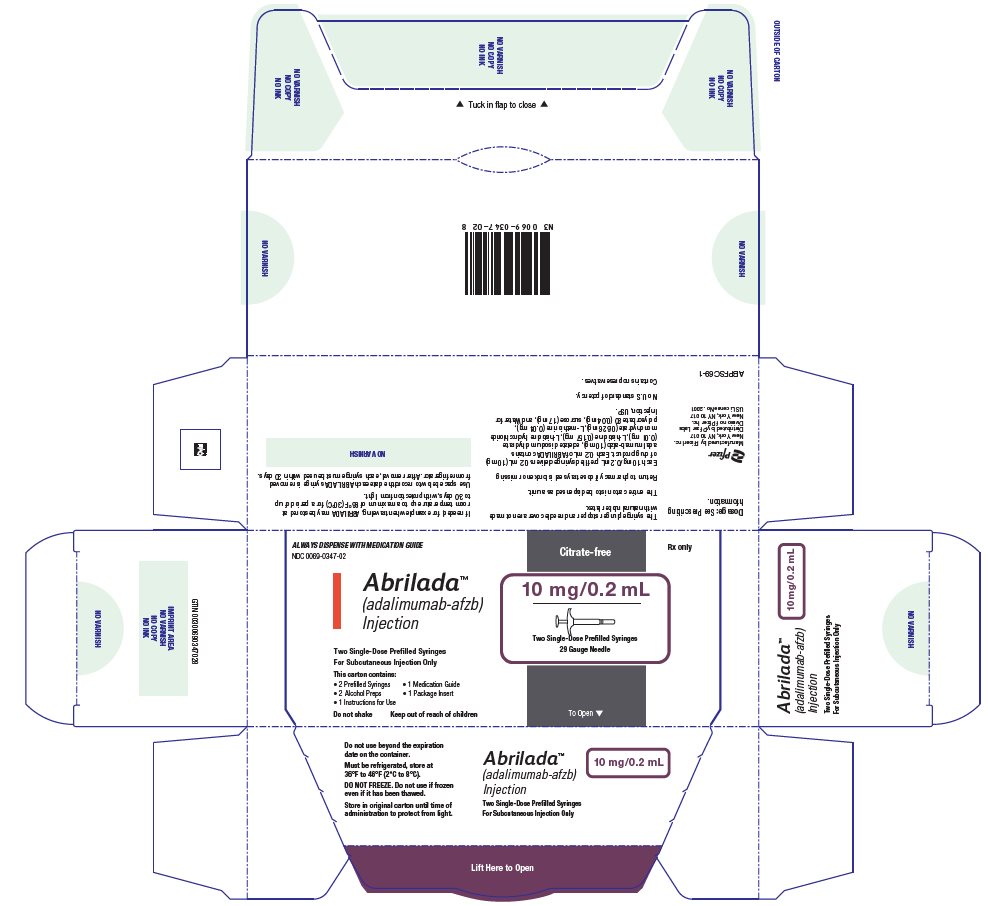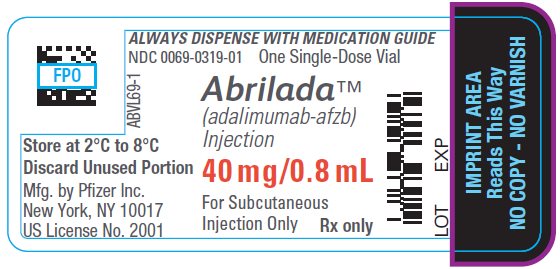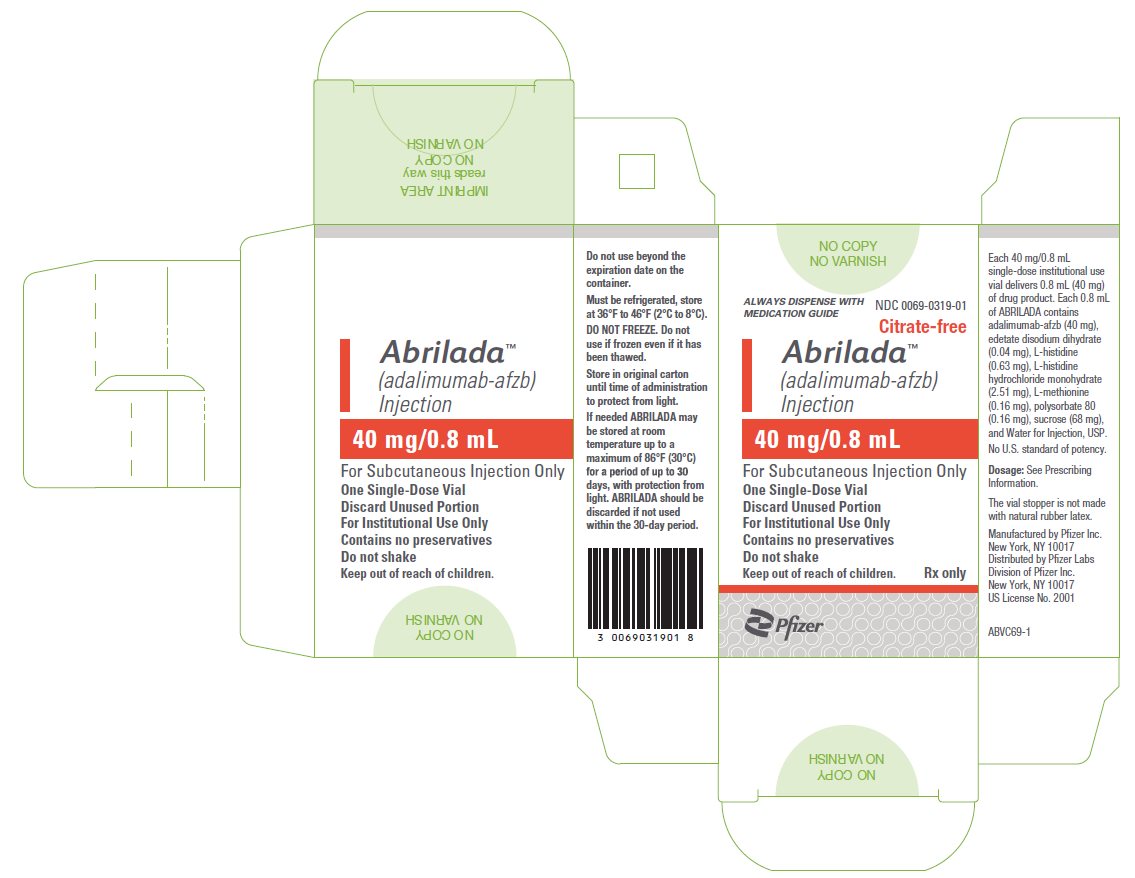 DRUG LABEL: ABRILADA
NDC: 0069-0325 | Form: KIT | Route: SUBCUTANEOUS
Manufacturer: Pfizer Laboratories Div Pfizer Inc
Category: prescription | Type: HUMAN PRESCRIPTION DRUG LABEL
Date: 20251222

ACTIVE INGREDIENTS: ADALIMUMAB 40 mg/0.8 mL; ISOPROPYL ALCOHOL 70 mL/100 mL
INACTIVE INGREDIENTS: EDETATE DISODIUM 0.04 mg/0.8 mL; HISTIDINE 0.63 mg/0.8 mL; HISTIDINE MONOHYDROCHLORIDE 2.51 mg/0.8 mL; METHIONINE 0.16 mg/0.8 mL; POLYSORBATE 80 0.16 mg/0.8 mL; SUCROSE 68 mg/0.8 mL; WATER; WATER

HIGHLIGHTS OF PRESCRIBING INFORMATION

These highlights do not include all the information needed to use ABRILADA safely and effectively. See full prescribing information for ABRILADA.
ABRILADA™ (adalimumab-afzb) injection, for subcutaneous use
Initial U.S. Approval: 2019
ABRILADA (adalimumab-afzb) is biosimilar [Biosimilar means that the biological product is approved based on data demonstrating that it is highly similar to an FDA-approved biological product, known as a reference product, and that there are no clinically meaningful differences between the biosimilar product and the reference product. Biosimilarity of ABRILADA has been demonstrated for the condition(s) of use (e.g., indication(s), dosing regimen(s)), strength(s), dosage form(s), and route(s) of administration described in its Full Prescribing Information.] to HUMIRA (adalimumab).

RECENT MAJOR CHANGES

Warnings and Precautions, Autoimmunity (5.9) | 12/2025

WARNING: SERIOUS INFECTIONS AND MALIGNANCY

See full prescribing information for complete boxed warning.

SERIOUS INFECTIONS (5.1, 6.1):

- Increased risk of serious infections leading to hospitalization or death, including tuberculosis (TB), bacterial sepsis, invasive fungal infections (such as histoplasmosis), and infections due to other opportunistic pathogens.
- Discontinue ABRILADA if a patient develops a serious infection or sepsis during treatment.
- Perform test for latent TB; if positive, start treatment for TB prior to starting ABRILADA.
- Monitor all patients for active TB during treatment, even if initial latent TB test is negative.

MALIGNANCY (5.2):

- Lymphoma and other malignancies, some fatal, have been reported in children and adolescent patients treated with TNF blockers including adalimumab products.
- Post‑marketing cases of hepatosplenic T‑cell lymphoma (HSTCL), a rare type of T‑cell lymphoma, have occurred in adolescent and young adults with inflammatory bowel disease treated with TNF blockers including adalimumab products.

1 INDICATIONS AND USAGE

ABRILADA is a tumor necrosis factor (TNF) blocker indicated for:

- Reducing signs and symptoms, inducing major clinical response, inhibiting the progression of structural damage, and improving physical function in adult patients with moderately to severely active rheumatoid arthritis. (1.1)
- Reducing signs and symptoms of moderately to severely active polyarticular juvenile idiopathic arthritis in patients 2 years of age and older. (1.2)
- Reducing signs and symptoms, inhibiting the progression of structural damage, and improving physical function in adult patients with active psoriatic arthritis. (1.3)
- Reducing signs and symptoms in adult patients with active ankylosing spondylitis. (1.4)
- Treatment of moderately to severely active Crohn’s disease in adults and pediatric patients 6 years of age and older. (1.5)
- Treatment of moderately to severely active ulcerative colitis in adult patients. (1.6)
  Limitations of Use: Effectiveness has not been established in patients who have lost response to or were intolerant to TNF blockers.
- Treatment of adult patients with moderate to severe chronic plaque psoriasis who are candidates for systemic therapy or phototherapy, and when other systemic therapies are medically less appropriate. (1.7)
- Treatment of moderate to severe hidradenitis suppurativa in adult patients. (1.8)
- Treatment of non-infectious intermediate, posterior, and panuveitis in adult patients. (1.9)

2 DOSAGE AND ADMINISTRATION

- Administer by subcutaneous injection (2)

Rheumatoid Arthritis, Psoriatic Arthritis, Ankylosing Spondylitis (2.2):

- Adults: 40 mg every other week.

Some patients with RA not receiving methotrexate may benefit from increasing the dosage to 40 mg every week or 80 mg every other week.

Juvenile Idiopathic Arthritis (2.3):

Pediatric Weight 2 Years of Age and Older | Recommended Dosage
10 kg (22 lbs) to less than 15 kg (33 lbs) | 10 mg every other week
15 kg (33 lbs) to less than 30 kg (66 lbs) | 20 mg every other week
30 kg (66 lbs) and greater | 40 mg every other week

Crohn's Disease (2.4):

- Adults: 160 mg on Day 1 (given in one day or split over two consecutive days); 80 mg on Day 15; and 40 mg every other week starting on Day 29.
- Pediatric Patients 6 Years of Age and Older:

Pediatric Weight | Recommended Dosage
Pediatric Weight | Days 1 and 15 | Starting on Day 29
17 kg (37 lbs) to less than 40 kg (88 lbs) | Day 1: 80 mg Day 15: 40 mg | 20 mg every other week
40 kg (88 lbs) and greater | Day 1: 160 mg (single dose or split over two consecutive days) Day 15: 80 mg | 40 mg every other week

Ulcerative Colitis (2.5):

- Adults: 160 mg on Day 1 (given in one day or split over two consecutive days), 80 mg on Day 15 and 40 mg every other week starting on Day 29. Discontinue in patients without evidence of clinical remission by eight weeks (Day 57).

Plaque Psoriasis or Adult Uveitis (2.6):

- Adults: 80 mg initial dose, followed by 40 mg every other week starting one week after initial dose.

Hidradenitis Suppurativa (2.7):

- Adults:
  - Day 1: 160 mg (given in one day or split over two consecutive days).
  - Day 15: 80 mg.
  - Day 29 and subsequent doses: 40 mg every week or 80 mg every other week.

3 DOSAGE FORMS AND STRENGTHS

Injection:

- Single-dose prefilled pen (ABRILADA Pen): 40 mg/0.8 mL (3)
- Single-dose prefilled glass syringe: 40 mg/0.8 mL, 20 mg/0.4 mL, 10 mg/0.2 mL (3)
- Single-dose glass vial for institutional use only: 40 mg/0.8 mL (3)

4 CONTRAINDICATIONS

None. (4)

5 WARNINGS AND PRECAUTIONS

- Serious infections: Do not start ABRILADA during an active infection. If an infection develops, monitor carefully, and stop ABRILADA if infection becomes serious. (5.1)
- Invasive fungal infections: For patients who develop a systemic illness on ABRILADA, consider empiric antifungal therapy for those who reside or travel to regions where mycoses are endemic. (5.1)
- Malignancies: Incidence of malignancies was greater in adalimumab-treated patients than in controls. (5.2)
- Anaphylaxis or serious hypersensitivity reactions may occur. (5.3)
- Hepatitis B virus reactivation: Monitor hepatitis B virus (HBV) carriers during and several months after therapy. If reactivation occurs, stop ABRILADA and begin anti-viral therapy. (5.4)
- Demyelinating disease: Exacerbation or new onset, may occur. (5.5)
- Cytopenias, pancytopenia: Advise patients to seek immediate medical attention if symptoms develop, and consider stopping ABRILADA. (5.6)
- Heart failure: Worsening or new onset, may occur. (5.8)
- Autoimmunity: Stop ABRILADA if lupus-like syndrome or autoimmune hepatitis develop. (5.9)

6 ADVERSE REACTIONS

Most common adverse reactions (>10%) are: infections (e.g. upper respiratory, sinusitis), injection site reactions, headache, and rash. (6.1)
To report SUSPECTED ADVERSE REACTIONS, contact Pfizer Inc. at 1-800-438-1985 or FDA at 1-800-FDA-1088 or www.fda.gov/medwatch.

7 DRUG INTERACTIONS

- Abatacept: Increased risk of serious infection. (5.1, 5.11, 7.2)
- Anakinra: Increased risk of serious infection. (5.1, 5.7, 7.2)
- Live vaccines: Avoid use with ABRILADA. (5.10, 7.3)

FULL PRESCRIBING INFORMATION

WARNING: SERIOUS INFECTIONS AND MALIGNANCY

SERIOUS INFECTIONS

Patients treated with adalimumab products, including ABRILADA are at increased risk for developing serious infections that may lead to hospitalization or death [see Warnings and Precautions (5.1)]. Most patients who developed these infections were taking concomitant immunosuppressants such as methotrexate or corticosteroids.

Discontinue ABRILADA if a patient develops a serious infection or sepsis.

Reported infections include:

- Active tuberculosis (TB), including reactivation of latent TB. Patients with TB have frequently presented with disseminated or extrapulmonary disease. Test patients for latent TB before ABRILADA use and during therapy. Initiate treatment for latent TB prior to ABRILADA use.
- Invasive fungal infections, including histoplasmosis, coccidioidomycosis, candidiasis, aspergillosis, blastomycosis, and pneumocystosis. Patients with histoplasmosis or other invasive fungal infections may present with disseminated, rather than localized, disease. Antigen and antibody testing for histoplasmosis may be negative in some patients with active infection. Consider empiric anti-fungal therapy in patients at risk for invasive fungal infections who develop severe systemic illness.
- Bacterial, viral and other infections due to opportunistic pathogens, including Legionella and Listeria.

Carefully consider the risks and benefits of treatment with ABRILADA prior to initiating therapy in patients with chronic or recurrent infection.

Monitor patients closely for the development of signs and symptoms of infection during and after treatment with ABRILADA, including the possible development of TB in patients who tested negative for latent TB infection prior to initiating therapy [see Warnings and Precautions (5.1) and Adverse Reactions (6.1)].

MALIGNANCY

Lymphoma and other malignancies, some fatal, have been reported in children and adolescent patients treated with TNF blockers including adalimumab products [see Warnings and Precautions (5.2)]. Post-marketing cases of hepatosplenic T-cell lymphoma (HSTCL), a rare type of T-cell lymphoma, have been reported in patients treated with TNF blockers including adalimumab products. These cases have had a very aggressive disease course and have been fatal. The majority of reported TNF blocker cases have occurred in patients with Crohn's disease or ulcerative colitis and the majority were in adolescent and young adult males. Almost all these patients had received treatment with azathioprine or 6-mercaptopurine (6–MP) concomitantly with a TNF blocker at or prior to diagnosis. It is uncertain whether the occurrence of HSTCL is related to use of a TNF blocker or a TNF blocker in combination with these other immunosuppressants [see Warnings and Precautions (5.2)].

1 INDICATIONS AND USAGE

1.1 Rheumatoid Arthritis

ABRILADA is indicated for reducing signs and symptoms, inducing major clinical response, inhibiting the progression of structural damage, and improving physical function in adult patients with moderately to severely active rheumatoid arthritis. ABRILADA can be used alone or in combination with methotrexate or other non-biologic disease-modifying anti-rheumatic drugs (DMARDs).

1.2 Juvenile Idiopathic Arthritis

ABRILADA is indicated for reducing signs and symptoms of moderately to severely active polyarticular juvenile idiopathic arthritis in patients 2 years of age and older. ABRILADA can be used alone or in combination with methotrexate.

1.3 Psoriatic Arthritis

ABRILADA is indicated for reducing signs and symptoms, inhibiting the progression of structural damage, and improving physical function in adult patients with active psoriatic arthritis. ABRILADA can be used alone or in combination with non-biologic DMARDs.

1.4 Ankylosing Spondylitis

ABRILADA is indicated for reducing signs and symptoms in adult patients with active ankylosing spondylitis.

1.5 Crohn's Disease

ABRILADA is indicated for the treatment of moderately to severely active Crohn's disease in adults and pediatric patients 6 years of age and older.

1.6 Ulcerative Colitis

ABRILADA is indicated for the treatment of moderately to severely active ulcerative colitis in adult patients.

Limitations of Use
The effectiveness of adalimumab products has not been established in patients who have lost response to or were intolerant to TNF blockers [see Clinical Studies (14.7)].

1.7 Plaque Psoriasis

ABRILADA is indicated for the treatment of adult patients with moderate to severe chronic plaque psoriasis who are candidates for systemic therapy or phototherapy, and when other systemic therapies are medically less appropriate. ABRILADA should only be administered to patients who will be closely monitored and have regular follow-up visits with a physician [see Warnings and Precautions (5)].

1.8 Hidradenitis Suppurativa

ABRILADA is indicated for the treatment of moderate to severe hidradenitis suppurativa in adult patients.

1.9 Uveitis

ABRILADA is indicated for the treatment of non-infectious intermediate, posterior, and panuveitis in adult patients.

2 DOSAGE AND ADMINISTRATION

2.1 Recommended Tuberculosis Evaluation

Prior to initiating ABRILADA and periodically during therapy, evaluate patients for active tuberculosis and test for latent infection [see Warnings and Precautions (5.1)].

2.2 Recommended Dosage in Rheumatoid Arthritis, Psoriatic Arthritis, and Ankylosing Spondylitis

The recommended subcutaneous dosage of ABRILADA for adult patients with rheumatoid arthritis (RA), psoriatic arthritis (PsA), or ankylosing spondylitis (AS) [see Indications and Usage (1.1, 1.3, 1.4)] is 40 mg administered every other week. Methotrexate (MTX), other non-biologic DMARDs, glucocorticoids, nonsteroidal anti-inflammatory drugs (NSAIDs), and/or analgesics may be continued during treatment with ABRILADA. In the treatment of RA, some patients not taking concomitant MTX may derive additional benefit from increasing the dosage of ABRILADA to 40 mg every week or 80 mg every other week.

2.3 Recommended Dosage in Juvenile Idiopathic Arthritis

The recommended subcutaneous dosage of ABRILADA for pediatric patients 2 years of age and older with polyarticular juvenile idiopathic arthritis (JIA) [see Indications and Usage (1.2)], based on weight, is shown below. MTX, glucocorticoids, NSAIDs, and/or analgesics may be continued during treatment with ABRILADA.

Pediatric Weight (2 years of age and older) | Recommended Dosage
10 kg (22 lbs) to less than 15 kg (33 lbs) | 10 mg every other week
15 kg (33 lbs) to less than 30 kg (66 lbs) | 20 mg every other week
30 kg (66 lbs) and greater | 40 mg every other week

Adalimumab products have not been studied in patients with polyarticular JIA less than 2 years of age or in patients with a weight below 10 kg.

2.4 Recommended Dosage in Crohn's Disease

Subcutaneous Adult Dosage Regimen

The recommended subcutaneous dosage of ABRILADA for adult patients with moderately to severely active Crohn's disease (CD) is 160 mg initially on Day 1 (given in one day or split over two consecutive days), followed by 80 mg two weeks later (Day 15). Two weeks later (Day 29) begin a dosage of 40 mg every other week. Aminosalicylates and/or corticosteroids may be continued during treatment with ABRILADA. Azathioprine, 6-mercaptopurine (6-MP) [see Warnings and Precautions (5.2)] or MTX may be continued during treatment with ABRILADA if necessary.

Subcutaneous Pediatric Dosage Regimen

The recommended subcutaneous dosage of ABRILADA for pediatric patients 6 years of age and older with moderately to severely active Crohn’s disease (CD), based on body weight, is shown below:

Pediatric Weight | Recommended Dosage
Pediatric Weight | Days 1 through 15 | Starting on Day 29
17 kg (37 lbs) to less than 40 kg (88 lbs) | Day 1: 80 mg Day 15: 40 mg | 20 mg every other week
40 kg (88 lbs) and greater | Day 1: 160 mg (single dose or split over two consecutive days) Day 15: 80 mg | 40 mg every other week

2.5 Recommended Dosage in Ulcerative Colitis

Subcutaneous Adult Dosage Regimen

The recommended subcutaneous dosage of ABRILADA for adult patients with moderately to severely active ulcerative colitis is 160 mg initially on Day 1 (given in one day or split over two consecutive days), followed by 80 mg two weeks later (Day 15). Two weeks later (Day 29) continue with a dosage of 40 mg every other week.

Discontinue ABRILADA in adult patients without evidence of clinical remission by eight weeks (Day 57) of therapy. Aminosalicylates and/or corticosteroids may be continued during treatment with ABRILADA. Azathioprine and 6-mercaptopurine (6-MP) [see Warnings and Precautions (5.2)] may be continued during treatment with ABRILADA if necessary.

2.6 Recommended Dosage in Plaque Psoriasis or Adults with Uveitis

The recommended subcutaneous dosage of ABRILADA for adult patients with plaque psoriasis (Ps) or uveitis (UV) [see Indications and Usage (1.7, 1.9)] is an initial dose of 80 mg, followed by 40 mg given every other week starting one week after the initial dose. The use of adalimumab products in moderate to severe chronic Ps beyond one year has not been evaluated in controlled clinical studies.

2.7 Recommended Dosage in Hidradenitis Suppurativa

Subcutaneous Adult Dosage Regimen

The recommended subcutaneous dosage of ABRILADA for adult patients with moderate to severe hidradenitis suppurativa (HS) is an initial dose of 160 mg (given in one day or split over two consecutive days), followed by 80 mg two weeks later (Day 15). Begin 40 mg weekly or 80 mg every other week dosing two weeks later (Day 29).

2.8 General Considerations for Administration

ABRILADA is intended for use under the guidance and supervision of a physician. A patient may self-inject ABRILADA or a caregiver may inject ABRILADA using either the ABRILADA pen or prefilled syringe if a physician determines that it is appropriate, and with medical follow-up, as necessary, after proper training in subcutaneous injection technique.

ABRILADA can be taken out of the refrigerator for 15 to 30 minutes before injecting to allow the liquid to come to room temperature. Do not remove the cap or cover while allowing it to reach room temperature. Carefully inspect the solution in the ABRILADA pen, prefilled syringe, or single-dose institutional use vial for particulate matter and discoloration prior to subcutaneous administration. If particulates or discolorations are noted, do not use the product. ABRILADA does not contain preservatives; therefore, discard unused portions of drug remaining from the syringe [see How Supplied/Storage and Handling (16)].

Instruct patients using the ABRILADA pen or prefilled syringe to inject the full amount in the syringe, according to the directions provided in the Instructions for Use [see Instructions for Use].

Injections should occur at separate sites in the thigh or abdomen. Rotate injection sites and do not give injections into areas where the skin is tender, bruised, red or hard.

If a dose is missed, administer the dose as soon as possible. Thereafter, resume dosing at the regular scheduled time.

The ABRILADA single-dose institutional use vial is for administration within an institutional setting only, such as a hospital, physician's office or clinic. Withdraw the dose using a sterile needle and syringe and administer promptly by a healthcare provider within an institutional setting. Only administer one dose per vial. The vial does not contain preservatives; therefore, discard unused portions.

3 DOSAGE FORMS AND STRENGTHS

ABRILADA is a clear and colorless to very light brown solution available as:

- Prefilled Pen (ABRILADA Pen)
  Injection: 40 mg/0.8 mL in a single-dose pen.
- Prefilled Syringe
  Injection: 40 mg/0.8 mL in a single-dose prefilled glass syringe.
  Injection: 20 mg/0.4 mL in a single-dose prefilled glass syringe.
  Injection: 10 mg/0.2 mL in a single-dose prefilled glass syringe.
- Single-Dose Institutional Use Vial
  Injection: 40 mg/0.8 mL in a single-dose glass vial for institutional use only.

4 CONTRAINDICATIONS

None.

5 WARNINGS AND PRECAUTIONS

5.1 Serious Infections

Patients treated with adalimumab products, including ABRILADA, are at increased risk for developing serious infections involving various organ systems and sites that may lead to hospitalization or death. Opportunistic infections due to bacterial, mycobacterial, invasive fungal, viral, parasitic, or other opportunistic pathogens including aspergillosis, blastomycosis, candidiasis, coccidioidomycosis, histoplasmosis, legionellosis, listeriosis, pneumocystosis, and tuberculosis have been reported with TNF blockers. Patients have frequently presented with disseminated rather than localized disease.

The concomitant use of a TNF blocker and abatacept or anakinra was associated with a higher risk of serious infections in patients with rheumatoid arthritis (RA); therefore, the concomitant use of ABRILADA and these biologic products is not recommended in the treatment of patients with RA [see Warnings and Precautions (5.7, 5.11) and Drug Interactions (7.2)].

Treatment with ABRILADA should not be initiated in patients with an active infection, including localized infections. Patients 65 years of age and older, patients with co-morbid conditions and/or patients taking concomitant immunosuppressants (such as corticosteroids or methotrexate), may be at greater risk of infection. Consider the risks and benefits of treatment prior to initiating therapy in patients:

- with chronic or recurrent infection;
- who have been exposed to tuberculosis;
- with a history of an opportunistic infection;
- who have resided or traveled in areas of endemic tuberculosis or endemic mycoses, such as histoplasmosis, coccidioidomycosis, or blastomycosis; or
- with underlying conditions that may predispose them to infection.

Tuberculosis

Cases of reactivation of tuberculosis and new onset tuberculosis infections have been reported in patients receiving adalimumab products, including patients who have previously received treatment for latent or active tuberculosis. Reports included cases of pulmonary and extrapulmonary (i.e., disseminated) tuberculosis. Evaluate patients for tuberculosis risk factors and test for latent infection prior to initiating ABRILADA and periodically during therapy.

Treatment of latent tuberculosis infection prior to therapy with TNF blocking agents has been shown to reduce the risk of tuberculosis reactivation during therapy. Prior to initiating ABRILADA, assess if treatment for latent tuberculosis is needed; and consider an induration of ≥5 mm a positive tuberculin skin test result, even for patients previously vaccinated with Bacille Calmette-Guerin (BCG).

Consider anti-tuberculosis therapy prior to initiation of ABRILADA in patients with a past history of latent or active tuberculosis in whom an adequate course of treatment cannot be confirmed, and for patients with a negative test for latent tuberculosis but having risk factors for tuberculosis infection. Despite prophylactic treatment for tuberculosis, cases of reactivated tuberculosis have occurred in patients treated with adalimumab products. Consultation with a physician with expertise in the treatment of tuberculosis is recommended to aid in the decision whether initiating anti-tuberculosis therapy is appropriate for an individual patient.

Strongly consider tuberculosis in the differential diagnosis in patients who develop a new infection during ABRILADA treatment, especially in patients who have previously or recently traveled to countries with a high prevalence of tuberculosis, or who have had close contact with a person with active tuberculosis.

Monitoring

Closely monitor patients for the development of signs and symptoms of infection during and after treatment with ABRILADA, including the development of tuberculosis in patients who tested negative for latent tuberculosis infection prior to initiating therapy. Tests for latent tuberculosis infection may also be falsely negative while on therapy with ABRILADA.

Discontinue ABRILADA if a patient develops a serious infection or sepsis. For a patient who develops a new infection during treatment with ABRILADA, closely monitor them, perform a prompt and complete diagnostic workup appropriate for an immunocompromised patient, and initiate appropriate antimicrobial therapy.

Invasive Fungal Infections

If patients develop a serious systemic illness and they reside or travel in regions where mycoses are endemic, consider invasive fungal infection in the differential diagnosis. Antigen and antibody testing for histoplasmosis may be negative in some patients with active infection. Consider appropriate empiric antifungal therapy, taking into account both the risk for severe fungal infection and the risks of antifungal therapy, while a diagnostic workup is being performed. To aid in the management of such patients, consider consultation with a physician with expertise in the diagnosis and treatment of invasive fungal infections.

5.2 Malignancies

Consider the risks and benefits of TNF-blocker treatment including ABRILADA prior to initiating therapy in patients with a known malignancy other than a successfully treated non-melanoma skin cancer (NMSC) or when considering continuing a TNF blocker in patients who develop a malignancy.

Malignancies in Adults

In the controlled portions of clinical trials of some TNF-blockers, including adalimumab products, more cases of malignancies have been observed among TNF-blocker-treated adult subjects compared to control-treated adult subjects. During the controlled portions of 39 global adalimumab clinical trials in adult subjects with rheumatoid arthritis (RA), psoriatic arthritis (PsA), ankylosing spondylitis (AS), Crohn's disease (CD), ulcerative colitis (UC), plaque psoriasis (Ps), hidradenitis suppurativa (HS) and uveitis (UV), malignancies, other than non-melanoma (basal cell and squamous cell) skin cancer, were observed at a rate (95% confidence interval) of 0.7 (0.48, 1.03) per 100 patient-years among 7973 adalimumab-treated subjects versus a rate of 0.7 (0.41, 1.17) per 100 patient-years among 4848 control-treated subjects (median duration of treatment of 4 months for adalimumab-treated subjects and 4 months for control-treated subjects). In 52 global controlled and uncontrolled clinical trials of adalimumab in adult patients with RA, PsA, AS, CD, UC, Ps, HS and UV, the most frequently observed malignancies, other than lymphoma and NMSC, were breast, colon, prostate, lung, and melanoma. The malignancies in adalimumab-treated subjects in the controlled and uncontrolled portions of the studies were similar in type and number to what would be expected in the general U.S. population according to the SEER database (adjusted for age, gender, and race).^1

In controlled trials of other TNF blockers in adult patients at higher risk for malignancies (i.e., subjects with COPD with a significant smoking history and cyclophosphamide-treated patients with Wegener's granulomatosis), a greater portion of malignancies occurred in the TNF blocker group compared to the control group.

Non-Melanoma Skin Cancer

During the controlled portions of 39 global adalimumab clinical trials in adult patients with RA, PsA, AS, CD, UC, Ps, HS and UV, the rate (95% confidence interval) of NMSC was 0.8 (0.52, 1.09) per 100 patient-years among adalimumab-treated subjects and 0.2 (0.10, 0.59) per 100 patient-years among control-treated subjects. Examine all patients, and in particular patients with a medical history of prior prolonged immunosuppressant therapy or psoriasis patients with a history of PUVA treatment for the presence of NMSC prior to and during treatment with ABRILADA.

Lymphoma and Leukemia

In the controlled portions of clinical trials of all the TNF-blockers in adults, more cases of lymphoma have been observed among TNF-blocker-treated subjects compared to control-treated subjects. In the controlled portions of 39 global adalimumab clinical trials in adult patients with RA, PsA, AS, CD, UC, Ps, HS and UV, 2 lymphomas occurred among 7973 adalimumab-treated subjects versus 1 among 4848 control-treated subjects. In 52 global controlled and uncontrolled clinical trials of adalimumab in adult patients with RA, PsA, AS, CD, UC, Ps, HS and UV with a median duration of approximately 0.7 years, including 24,605 subjects and over 40,215 patient-years of adalimumab, the observed rate of lymphomas was approximately 0.11 per 100 patient-years. This is approximately three-fold higher than expected in the general U.S. population according to the SEER database (adjusted for age, gender, and race).^1 Rates of lymphoma in clinical trials of adalimumab cannot be compared to rates of lymphoma in clinical trials of other TNF blockers and may not predict the rates observed in a broader patient population. Patients with RA and other chronic inflammatory diseases, particularly those with highly active disease and/or chronic exposure to immunosuppressant therapies, may be at a higher risk (up to several fold) than the general population for the development of lymphoma, even in the absence of TNF blockers. Post-marketing cases of acute and chronic leukemia have been reported in association with TNF-blocker use in RA and other indications. Even in the absence of TNF-blocker therapy, patients with RA may be at a higher risk (approximately two-fold) than the general population for the development of leukemia.

Malignancies in Pediatric Patients and Young Adults

Malignancies, some fatal, have been reported among children, adolescents, and young adults who received treatment with TNF-blockers (initiation of therapy ≤18 years of age), of which ABRILADA is a member. Approximately half the cases were lymphomas, including Hodgkin's and non-Hodgkin's lymphoma. The other cases represented a variety of different malignancies and included rare malignancies usually associated with immunosuppression and malignancies that are not usually observed in children and adolescents. The malignancies occurred after a median of 30 months of therapy (range 1 to 84 months). Most of the patients were receiving concomitant immunosuppressants. These cases were reported post-marketing and are derived from a variety of sources including registries and spontaneous postmarketing reports.

Postmarketing cases of hepatosplenic T-cell lymphoma (HSTCL), a rare type of T-cell lymphoma, have been reported in patients treated with TNF blockers including adalimumab products. These cases have had a very aggressive disease course and have been fatal. The majority of reported TNF blocker cases have occurred in patients with Crohn's disease or ulcerative colitis and the majority were in adolescent and young adult males. Almost all of these patients had received treatment with the immunosuppressants azathioprine or 6-mercaptopurine (6–MP) concomitantly with a TNF blocker at or prior to diagnosis. It is uncertain whether the occurrence of HSTCL is related to use of a TNF blocker or a TNF blocker in combination with these other immunosuppressants. The potential risk with the combination of azathioprine or 6-mercaptopurine and ABRILADA should be carefully considered.

5.3 Hypersensitivity Reactions

Anaphylaxis and angioneurotic edema have been reported following administration of adalimumab products. If an anaphylactic or other serious allergic reaction occurs, immediately discontinue administration of ABRILADA and institute appropriate therapy. In clinical trials of adalimumab, hypersensitivity reactions (e.g., rash, anaphylactoid reaction, fixed drug reaction, non-specified drug reaction, urticaria) have been observed.

5.4 Hepatitis B Virus Reactivation

Use of TNF blockers, including ABRILADA, may increase the risk of reactivation of hepatitis B virus (HBV) in patients who are chronic carriers of this virus. In some instances, HBV reactivation occurring in conjunction with TNF blocker therapy has been fatal. The majority of these reports have occurred in patients concomitantly receiving other medications that suppress the immune system, which may also contribute to HBV reactivation. Evaluate patients at risk for HBV infection for prior evidence of HBV infection before initiating TNF blocker therapy. Exercise caution in prescribing TNF blockers for patients identified as carriers of HBV. Adequate data are not available on the safety or efficacy of treating patients who are carriers of HBV with anti-viral therapy in conjunction with TNF blocker therapy to prevent HBV reactivation. For patients who are carriers of HBV and require treatment with TNF blockers, closely monitor such patients for clinical and laboratory signs of active HBV infection throughout therapy and for several months following termination of therapy. In patients who develop HBV reactivation, stop ABRILADA and initiate effective anti-viral therapy with appropriate supportive treatment. The safety of resuming TNF blocker therapy after HBV reactivation is controlled is not known. Therefore, exercise caution when considering resumption of ABRILADA therapy in this situation and monitor patients closely.

5.5 Neurologic Reactions

Use of TNF blocking agents, including adalimumab products, has been associated with rare cases of new onset or exacerbation of clinical symptoms and/or radiographic evidence of central nervous system demyelinating disease, including multiple sclerosis (MS) and optic neuritis, and peripheral demyelinating disease, including Guillain-Barré syndrome. Exercise caution in considering the use of ABRILADA in patients with preexisting or recent-onset central or peripheral nervous system demyelinating disorders; discontinuation of ABRILADA should be considered if any of these disorders develop. There is a known association between intermediate uveitis and central demyelinating disorders.

5.6 Hematological Reactions

Rare reports of pancytopenia including aplastic anemia have been reported with TNF blocking agents. Adverse reactions of the hematologic system, including medically significant cytopenia (e.g., thrombocytopenia, leukopenia) have been infrequently reported with adalimumab products. The causal relationship of these reports to adalimumab products remains unclear. Advise all patients to seek immediate medical attention if they develop signs and symptoms suggestive of blood dyscrasias or infection (e.g., persistent fever, bruising, bleeding, pallor) while on ABRILADA. Consider discontinuation of ABRILADA therapy in patients with confirmed significant hematologic abnormalities.

5.7 Increased Risk of Infection When Used with Anakinra

Concurrent use of anakinra (an interleukin-1 antagonist) and another TNF-blocker, was associated with a greater proportion of serious infections and neutropenia and no added benefit compared with the TNF-blocker alone in patients with RA. Therefore, the combination of ABRILADA and anakinra is not recommended [see Drug Interactions (7.2)].

5.8 Heart Failure

Cases of worsening congestive heart failure (CHF) and new onset CHF have been reported with TNF blockers. Cases of worsening CHF have also been observed with adalimumab products. Adalimumab products have not been formally studied in patients with CHF; however, in clinical trials of another TNF blocker, a higher rate of serious CHF-related adverse reactions was observed. Exercise caution when using ABRILADA in patients who have heart failure and monitor them carefully.

5.9 Autoimmunity

Treatment with adalimumab products may result in the formation of autoantibodies and, rarely, in the development of a lupus-like syndrome or autoimmune hepatitis [see Adverse Reactions (6.1, 6.3)]. If a patient develops symptoms and findings suggestive of a lupus‑like syndrome or autoimmune hepatitis following treatment with ABRILADA, discontinue treatment and evaluate the patient.

5.10 Immunizations

In a placebo-controlled clinical trial of patients with RA, no difference was detected in anti-pneumococcal antibody response between adalimumab and placebo treatment groups when the pneumococcal polysaccharide vaccine and influenza vaccine were administered concurrently with adalimumab. Similar proportions of subjects developed protective levels of anti-influenza antibodies between adalimumab and placebo treatment groups; however, titers in aggregate to influenza antigens were moderately lower in patients receiving adalimumab. The clinical significance of this is unknown. Patients on ABRILADA may receive concurrent vaccinations, except for live vaccines. No data are available on the secondary transmission of infection by live vaccines in patients receiving adalimumab products.

It is recommended that pediatric patients, if possible, be brought up to date with all immunizations in agreement with current immunization guidelines prior to initiating ABRILADA therapy. Patients on ABRILADA may receive concurrent vaccinations, except for live vaccines.

The safety of administering live or live-attenuated vaccines in infants exposed to adalimumab products in utero is unknown. Risks and benefits should be considered prior to vaccinating (live or live-attenuated) exposed infants [see Use in Specific Populations (8.1, 8.4)].

5.11 Increased Risk of Infection When Used with Abatacept

In controlled trials, the concurrent administration of TNF-blockers and abatacept was associated with a greater proportion of serious infections than the use of a TNF-blocker alone; the combination therapy, compared to the use of a TNF-blocker alone, has not demonstrated improved clinical benefit in the treatment of RA. Therefore, the combination of abatacept with TNF-blockers including ABRILADA is not recommended [see Drug Interactions (7.2)].

6 ADVERSE REACTIONS

The following clinically significant adverse reactions are described elsewhere in the labeling:

- Serious Infections [see Warnings and Precautions (5.1)]
- Malignancies [see Warnings and Precautions (5.2)]
- Hypersensitivity Reactions [see Warnings and Precautions (5.3)]
- Hepatitis B Virus Reactivation [see Warnings and Precautions (5.4)]
- Neurologic Reactions [see Warnings and Precautions (5.5)]
- Hematological Reactions [see Warnings and Precautions (5.6)]
- Heart Failure [see Warnings and Precautions (5.8)]
- Autoimmunity [see Warnings and Precautions (5.9)]

6.1 Clinical Trials Experience

Because clinical trials are conducted under widely varying conditions, adverse reaction rates observed in the clinical trials of a drug cannot be directly compared to rates in the clinical trials of another drug and may not reflect the rates observed in practice.

The most common adverse reaction with adalimumab was injection site reactions. In placebo-controlled trials, 20% of subjects treated with adalimumab developed injection site reactions (erythema and/or itching, hemorrhage, pain or swelling), compared to 14% of subjects receiving placebo. Most injection site reactions were described as mild and generally did not necessitate drug discontinuation.

The proportion of subjects who discontinued treatment due to adverse reactions during the double-blind, placebo-controlled portion of studies in subjects with RA (i.e., Studies RA-I, RA-II, RA-III and RA-IV) was 7% for subjects taking adalimumab and 4% for placebo-treated subjects. The most common adverse reactions leading to discontinuation of adalimumab in these RA studies were clinical flare reaction (0.7%), rash (0.3%) and pneumonia (0.3%).

Infections

In the controlled portions of the 39 global adalimumab clinical trials in adult subjects with RA, PsA, AS, CD, UC, Ps, HS and UV, the rate of serious infections was 4.3 per 100 patient-years in 7973 adalimumab-treated subjects versus a rate of 2.9 per 100 patient-years in 4848 control-treated subjects. Serious infections observed included pneumonia, septic arthritis, prosthetic and post-surgical infections, erysipelas, cellulitis, diverticulitis, and pyelonephritis [see Warnings and Precautions (5.1)].

Tuberculosis and Opportunistic Infections

In 52 global controlled and uncontrolled clinical trials in RA, PsA, AS, CD, UC, Ps, HS and UV that included 24,605 adalimumab-treated subjects, the rate of reported active tuberculosis was 0.20 per 100 patient-years and the rate of positive PPD conversion was 0.09 per 100 patient-years. In a subgroup of 10,113 U.S. and Canadian adalimumab-treated subjects, the rate of reported active TB was 0.05 per 100 patient-years and the rate of positive PPD conversion was 0.07 per 100 patient-years. These trials included reports of miliary, lymphatic, peritoneal, and pulmonary TB. Most of the TB cases occurred within the first eight months after initiation of therapy and may reflect recrudescence of latent disease. In these global clinical trials, cases of serious opportunistic infections have been reported at an overall rate of 0.05 per 100 patient-years. Some cases of serious opportunistic infections and TB have been fatal [see Warnings and Precautions (5.1)].

Autoantibodies

In the rheumatoid arthritis controlled trials, 12% of subjects treated with adalimumab and 7% of placebo-treated subjects that had negative baseline ANA titers developed positive titers at Week 24. Two subjects out of 3046 treated with adalimumab developed clinical signs suggestive of new-onset lupus-like syndrome. The subjects improved following discontinuation of therapy. No subjects developed lupus nephritis or central nervous system symptoms. The impact of long-term treatment with adalimumab products on the development of autoimmune diseases is unknown.

Liver Enzyme Elevations

There have been reports of severe hepatic reactions including acute liver failure in subjects receiving TNF-blockers. In controlled Phase 3 trials of adalimumab (40 mg SC every other week) in subjects with RA, PsA, and AS with control period duration ranging from 4 to 104 weeks, ALT elevations ≥3 × ULN occurred in 3.5% of adalimumab-treated subjects and 1.5% of control-treated subjects. Since many of these subjects in these trials were also taking medications that cause liver enzyme elevations (e.g., NSAIDs, MTX), the relationship between adalimumab and the liver enzyme elevations is not clear. In a controlled Phase 3 trial of adalimumab in subjects with polyarticular JIA who were 4 to 17 years, ALT elevations ≥3 × ULN occurred in 4.4% of adalimumab-treated subjects and 1.5% of control-treated subjects (ALT more common than AST); liver enzyme test elevations were more frequent among those treated with the combination of adalimumab and MTX than those treated with adalimumab alone. In general, these elevations did not lead to discontinuation of adalimumab treatment. No ALT elevations ≥3 × ULN occurred in the open-label study of adalimumab in subjects with polyarticular JIA who were 2 to <4 years.

In controlled Phase 3 trials of adalimumab (initial doses of 160 mg and 80 mg, or 80 mg and 40 mg on Days 1 and 15, respectively, followed by 40 mg every other week) in adult subjects with Crohn's Disease with a control period duration ranging from 4 to 52 weeks, ALT elevations ≥3 × ULN occurred in 0.9% of adalimumab-treated subjects and 0.9% of control-treated subjects. In the Phase 3 trial of adalimumab in pediatric subjects with Crohn's disease which evaluated efficacy and safety of two body weight based maintenance dose regimens following body weight based induction therapy up to 52 weeks of treatment, ALT elevations ≥3 × ULN occurred in 2.6% (5/192) of subjects, of whom 4 were receiving concomitant immunosuppressants at baseline; none of these subjects discontinued due to abnormalities in ALT tests. In controlled Phase 3 trials of adalimumab (initial doses of 160 mg and 80 mg on Days 1 and 15 respectively, followed by 40 mg every other week) in adult subjects with UC with control period duration ranging from 1 to 52 weeks, ALT elevations ≥3 × ULN occurred in 1.5% of adalimumab-treated subjects and 1.0% of control-treated subjects. In controlled Phase 3 trials of adalimumab (initial dose of 80 mg then 40 mg every other week) in subjects with Ps with control period duration ranging from 12 to 24 weeks, ALT elevations ≥3 × ULN occurred in 1.8% of adalimumab-treated subjects and 1.8% of control-treated subjects. In controlled trials of adalimumab (initial doses of 160 mg at Week 0 and 80 mg at Week 2, followed by 40 mg every week starting at Week 4), in subjects with HS with a control period duration ranging from 12 to 16 weeks, ALT elevations ≥3 x ULN occurred in 0.3% of adalimumab-treated subjects and 0.6% of control-treated subjects. In controlled trials of adalimumab (initial doses of 80 mg at Week 0 followed by 40 mg every other week starting at Week 1) in adult subjects with uveitis with an exposure of 165.4 PYs and 119.8 PYs in adalimumab-treated and control-treated subjects, respectively, ALT elevations ≥3 x ULN occurred in 2.4% of adalimumab-treated subjects and 2.4% of control-treated subjects.

Other Adverse Reactions

Rheumatoid Arthritis Clinical Studies

The data described below reflect exposure to adalimumab in 2468 subjects, including 2073 exposed for 6 months, 1497 exposed for greater than one year and 1380 in adequate and well-controlled studies (Studies RA-I, RA-II, RA-III, and RA-IV). Adalimumab was studied primarily in placebo-controlled trials and in long-term follow up studies for up to 36 months duration. The population had a mean age of 54 years, 77% were female, 91% were Caucasian and had moderately to severely active rheumatoid arthritis. Most subjects received 40 mg adalimumab every other week [see Clinical Studies (14.1)].

Table 1 summarizes reactions reported at a rate of at least 5% in subjects treated with adalimumab 40 mg every other week compared to placebo and with an incidence higher than placebo. In Study RA-III, the types and frequencies of adverse reactions in the second year open-label extension were similar to those observed in the one-year double-blind portion.

Table 1. Adverse Reactions Reported by ≥5% of Subjects Treated with Adalimumab During Placebo-Controlled Period of Pooled RA Studies (Studies RA-I, RA-II, RA-III, and RA-IV)
Adverse Reaction (Preferred Term) | Adalimumab 40 mg Subcutaneous Every Other Week (N=705) | Placebo (N=690)
Respiratory
Upper respiratory infection | 17% | 13%
Sinusitis | 11% | 9%
Flu syndrome | 7% | 6%
Gastrointestinal
Nausea | 9% | 8%
Abdominal pain | 7% | 4%
Laboratory Tests [Laboratory test abnormalities were reported as adverse reactions in European trials.]
Laboratory test abnormal | 8% | 7%
Hypercholesterolemia | 6% | 4%
Hyperlipidemia | 7% | 5%
Hematuria | 5% | 4%
Alkaline phosphatase increased | 5% | 3%
Other
Headache | 12% | 8%
Rash | 12% | 6%
Accidental injury | 10% | 8%
Injection site reaction [Does not include injection site erythema, itching, hemorrhage, pain, or swelling.] | 8% | 1%
Back pain | 6% | 4%
Urinary tract infection | 8% | 5%
Hypertension | 5% | 3%

Less Common Adverse Reactions in Rheumatoid Arthritis Clinical Studies

Other infrequent serious adverse reactions that do not appear in the Warnings and Precautions or Adverse Reaction sections that occurred at an incidence of less than 5% in adalimumab-treated subjects in RA studies (RA-I, RA-II, RA-III, and RA-IV) were:

- Body as a Whole: Pain in extremity, pelvic pain, surgery, thorax pain
- Cardiovascular System: Arrhythmia, atrial fibrillation, chest pain, coronary artery disorder, heart arrest, hypertensive encephalopathy, myocardial infarct, palpitation, pericardial effusion, pericarditis, syncope, tachycardia
- Digestive System: Cholecystitis, cholelithiasis, esophagitis, gastroenteritis, gastrointestinal hemorrhage, hepatic necrosis, vomiting
- Endocrine System: Parathyroid disorder
- Hemic and Lymphatic System: Agranulocytosis, polycythemia
- Metabolic and Nutritional Disorders: Dehydration, healing abnormal, ketosis, paraproteinemia, peripheral edema
- Musculo-Skeletal System: Arthritis, bone disorder, bone fracture (not spontaneous), bone necrosis, joint disorder, muscle cramps, myasthenia, pyogenic arthritis, synovitis, tendon disorder
- Neoplasia: Adenoma
- Nervous System: Confusion, paresthesia, subdural hematoma, tremor
- Respiratory System: Asthma, bronchospasm, dyspnea, lung function decreased, pleural effusion
- Special Senses: Cataract
- Thrombosis: Thrombosis leg
- Urogenital System: Cystitis, kidney calculus, menstrual disorder

Juvenile Idiopathic Arthritis Clinical Studies

In general, the adverse reactions in the adalimumab-treated subjects in the polyarticular juvenile idiopathic arthritis (JIA) trials (Studies JIA-I and JIA-II) [see Clinical Studies (14.2)] were similar in frequency and type to those seen in adult subjects [see Warnings and Precautions (5), Adverse Reactions (6)]. Important findings and differences from adults are discussed in the following paragraphs.

In Study JIA-I, adalimumab was studied in 171 subjects who were 4 to 17 years of age, with polyarticular JIA. Severe adverse reactions reported in the study included neutropenia, streptococcal pharyngitis, increased aminotransferases, herpes zoster, myositis, metrorrhagia, and appendicitis. Serious infections were observed in 4% of subjects within approximately 2 years of initiation of treatment with adalimumab and included cases of herpes simplex, pneumonia, urinary tract infection, pharyngitis, and herpes zoster.

In Study JIA-I, 45% of subjects experienced an infection while receiving adalimumab with or without concomitant MTX in the first 16 weeks of treatment. The types of infections reported in adalimumab-treated subjects were generally similar to those commonly seen in polyarticular JIA subjects who are not treated with TNF blockers. Upon initiation of treatment, the most common adverse reactions occurring in this population treated with adalimumab were injection site pain and injection site reaction (19% and 16%, respectively). A less commonly reported adverse event in subjects receiving adalimumab was granuloma annulare which did not lead to discontinuation of adalimumab treatment.

In the first 48 weeks of treatment in Study JIA-I, non-serious hypersensitivity reactions were seen in approximately 6% of subjects and included primarily localized allergic hypersensitivity reactions and allergic rash.

In Study JIA-I, 10% of subjects treated with adalimumab who had negative baseline anti-dsDNA antibodies developed positive titers after 48 weeks of treatment. No subject developed clinical signs of autoimmunity during the clinical trial.

Approximately 15% of subjects treated with adalimumab developed mild-to-moderate elevations of creatine phosphokinase (CPK) in Study JIA-I. Elevations exceeding 5 times the upper limit of normal were observed in several subjects. CPK concentrations decreased or returned to normal in all subjects. Most subjects were able to continue adalimumab without interruption.

In Study JIA-II, adalimumab was studied in 32 subjects who were 2 to <4 years of age or 4 years of age and older weighing <15 kg with polyarticular JIA. The safety profile for this population was similar to the safety profile seen in subjects 4 to 17 years of age with polyarticular JIA.

In Study JIA-II, 78% of subjects experienced an infection while receiving adalimumab. These included nasopharyngitis, bronchitis, upper respiratory tract infection, otitis media, and were mostly mild to moderate in severity. Serious infections were observed in 9% of subjects receiving adalimumab in the study and included dental caries, rotavirus gastroenteritis, and varicella.

In Study JIA-II, non-serious allergic reactions were observed in 6% of subjects and included intermittent urticaria and rash, which were all mild in severity.

Psoriatic Arthritis and Ankylosing Spondylitis Clinical Studies

Adalimumab has been studied in 395 subjects with psoriatic arthritis (PsA) in two placebo-controlled trials and in an open-label study and in 393 subjects with ankylosing spondylitis (AS) in two placebo-controlled studies [see Clinical Studies (14.3, 14.4)]. The safety profile for subjects with PsA and AS treated with adalimumab 40 mg every other week was similar to the safety profile seen in subjects with RA, adalimumab Studies RA-I through IV.

Crohn's Disease Clinical Studies

Adults: The safety profile of adalimumab in 1478 adult subjects with Crohn's disease from four placebo-controlled and two open-label extension studies [see Clinical Studies (14.5)] was similar to the safety profile seen in subjects with RA.

Pediatric Patients 6 Years to 17 Years: The safety profile of adalimumab in 192 pediatric subjects from one double-blind study (Study PCD-I) and one open-label extension study [see Clinical Studies (14.6)] was similar to the safety profile seen in adult subjects with Crohn's disease.

During the 4-week open-label induction phase of Study PCD-I, the most common adverse reactions occurring in the pediatric population treated with adalimumab were injection site pain and injection site reaction (6% and 5%, respectively).

A total of 67% of children experienced an infection while receiving adalimumab in Study PCD-I.
These included upper respiratory tract infection and nasopharyngitis.

A total of 5% of children experienced a serious infection while receiving adalimumab in Study PCD-I. These included viral infection, device related sepsis (catheter), gastroenteritis, H1N1 influenza, and disseminated histoplasmosis.

In Study PCD-I, allergic reactions were observed in 5% of children which were all non-serious and were primarily localized reactions.

Ulcerative Colitis Clinical Studies

Adults: The safety profile of adalimumab in 1010 adult subjects with ulcerative colitis (UC) from two placebo-controlled studies and one open-label extension study [see Clinical Studies (14.7)] was similar to the safety profile seen in subjects with RA.

Plaque Psoriasis Clinical Studies

Adalimumab has been studied in 1696 subjects with plaque psoriasis (Ps) in placebo-controlled and open-label extension studies [see Clinical Studies (14.8)]. The safety profile for subjects with Ps treated with adalimumab was similar to the safety profile seen in subjects with RA with the following exceptions. In the placebo-controlled portions of the clinical trials in Ps subjects, adalimumab-treated subjects had a higher incidence of arthralgia when compared to controls (3% vs. 1%).

Hidradenitis Suppurativa Clinical Studies

Adalimumab has been studied in 727 subjects with hidradenitis suppurativa (HS) in three placebo-controlled studies and one open-label extension study [see Clinical Studies (14.9)]. The safety profile for subjects with HS treated with adalimumab weekly was consistent with the known safety profile of adalimumab.

Flare of HS, defined as ≥25% increase from baseline in abscesses and inflammatory nodule counts and with a minimum of 2 additional lesions, was documented in 22 (22%) of the 100 subjects who were withdrawn from adalimumab treatment following the primary efficacy timepoint in two studies.

Uveitis Clinical Studies

Adalimumab has been studied in 464 adult subjects with uveitis (UV) in placebo-controlled and open-label extension studies [see Clinical Studies (14.10)]. The safety profile for subjects with UV treated with adalimumab was similar to the safety profile seen in subjects with RA.

6.2 Immunogenicity

The observed incidence of anti-drug antibodies is highly dependent on the sensitivity and specificity of the assay. Differences in assay methods preclude meaningful comparisons of the incidence of anti-drug antibodies in the studies described below with the incidence of anti-drug antibodies in other studies, including those of adalimumab or of other adalimumab products.

There are two assays that have been used to measure anti-adalimumab antibodies. With the ELISA, antibodies to adalimumab could be detected only when serum adalimumab concentrations were <2 mcg/mL. The ECL assay can detect anti-adalimumab antibody titers independent of adalimumab concentrations in the serum samples. The incidence of anti-adalimumab antibody (AAA) development in patients treated with adalimumab are presented in Table 2.

Table 2. Anti-Adalimumab Antibody Development Determined by ELISA and ECL Assay in Patients Treated with Adalimumab
Indications |  | Study Duration | Anti-Adalimumab Antibody Incidence by ELISA (n/N) |  | Anti-Adalimumab Antibody Incidence by ECL Assay (n/N)
Indications |  | Study Duration | In all patients who received adalimumab | In patients with serum adalimumab concentrations <2 mcg/mL
Rheumatoid Arthritis [In patients receiving concomitant methotrexate (MTX), the incidence of anti-adalimumab antibody was 1% compared to 12% with adalimumab monotherapy.] |  | 6 to 12 months | 5% (58/1062) | NR | NA
Juvenile Idiopathic Arthritis (JIA) | 4 to 17 years of age [In patients receiving concomitant MTX, the incidence of anti-adalimumab antibody was 6% compared to 26% with adalimumab monotherapy.] | 48 weeks | 16% (27/171) | NR | NA
Juvenile Idiopathic Arthritis (JIA) | 2 to 4 years of age or ≥4 years of age and weighing <15 kg | 24 weeks | 7% (1/15) [This patient received concomitant MTX.] | NR | NA
Psoriatic Arthritis [In patients receiving concomitant MTX, the incidence of antibody development was 7% compared to 1% in RA.] |  | 48 weeks [Subjects enrolled after completing 2 previous studies of 24 weeks or 12 weeks of treatments.] | 13% (24/178) | NR | NA
Ankylosing Spondylitis |  | 24 weeks | 9% (16/185) | NR | NA
Adult Crohn's Disease |  | 56 weeks | 3% (7/269) | 8% (7/86) | NA
Pediatric Crohn's Disease |  | 52 weeks | 3% (6/182) | 10% (6/58) | NA
Adult Ulcerative Colitis |  | 52 weeks | 5% (19/360) | 21% (19/92) | NA
Plaque Psoriasis [In plaque psoriasis patients who were on adalimumab monotherapy and subsequently withdrawn from the treatment, the rate of antibodies to adalimumab after retreatment was similar to the rate observed prior to withdrawal.] |  | Up to 52 weeks [One 12-week Phase 2 study and one 52-week Phase 3 study.] | 8% (77/920) | 21% (77/372) | NA
Hidradenitis Suppurativa |  | 36 weeks | 7% (30/461) | 28% (58/207) [Among subjects in the 2 Phase 3 studies who stopped adalimumab treatment for up to 24 weeks and in whom adalimumab serum levels subsequently declined to <2 mcg/mL (approximately 22% of total subjects studied).] | 61% (272/445) [No apparent association between antibody development and safety was observed.]
Non-infectious Uveitis |  | 52 weeks | 5% (12/249) | 21% (12/57) | 40% (99/249) [No correlation of antibody development to safety or efficacy outcomes was observed.]
n: number of patients with anti-adalimumab antibody; NR: not reported; NA: Not applicable (not performed).

Rheumatoid Arthritis and Psoriatic Arthritis: Subjects in Studies RA-I, RA-II, and RA-III were tested at multiple time points for antibodies to adalimumab using the ELISA during the 6- to 12-month period. No apparent correlation of antibody development to adverse reactions was observed. With monotherapy, subjects receiving every other week dosing may develop antibodies more frequently than those receiving weekly dosing. In subjects receiving the recommended dosage of 40 mg every other week as monotherapy, the ACR 20 response was lower among antibody-positive subjects than among antibody-negative subjects. The long-term immunogenicity of adalimumab products is unknown.

6.3 Postmarketing Experience

The following adverse reactions have been identified during post-approval use of adalimumab products. Because these reactions are reported voluntarily from a population of uncertain size, it is not always possible to reliably estimate their frequency or establish a causal relationship to adalimumab products exposure.

- Gastrointestinal disorders: Diverticulitis, large bowel perforations including perforations associated with diverticulitis and appendiceal perforations associated with appendicitis, pancreatitis
- General disorders and administration site conditions: Pyrexia
- Hepato-biliary disorders: Liver failure, hepatitis, autoimmune hepatitis
- Immune system disorders: Sarcoidosis
- Neoplasms benign, malignant and unspecified (including cysts and polyps): Merkel Cell Carcinoma (neuroendocrine carcinoma of the skin)
- Nervous system disorders: Demyelinating disorders (e.g., optic neuritis, Guillain-Barré syndrome), cerebrovascular accident
- Respiratory disorders: Interstitial lung disease, including pulmonary fibrosis, pulmonary embolism
- Skin reactions: Stevens Johnson Syndrome, cutaneous vasculitis, erythema multiforme, new or worsening psoriasis (all sub-types including pustular and palmoplantar), alopecia, lichenoid skin reaction
- Vascular disorders: Systemic vasculitis, deep vein thrombosis

7 DRUG INTERACTIONS

7.1 Methotrexate

Adalimumab has been studied in rheumatoid arthritis (RA) patients taking concomitant methotrexate (MTX). Although MTX reduced the apparent clearance of adalimumab, the data do not suggest the need for dose adjustment of either ABRILADA or MTX [see Clinical Pharmacology (12.3)].

7.2 Biological Products

In clinical studies in patients with RA, an increased risk of serious infections has been observed with the combination of TNF blockers with anakinra or abatacept, with no added benefit; therefore, use of ABRILADA with abatacept or anakinra is not recommended in patients with RA [see Warnings and Precautions (5.7, 5.11)]. A higher rate of serious infections has also been observed in patients with RA treated with rituximab who received subsequent treatment with a TNF blocker. There is insufficient information regarding the concomitant use of ABRILADA and other biologic products for the treatment of RA, PsA, AS, CD, UC, Ps, HS and UV. Concomitant administration of ABRILADA with other biologic DMARDs (e.g., anakinra and abatacept) or other TNF blockers is not recommended based upon the possible increased risk for infections and other potential pharmacological interactions.

7.3 Live Vaccines

Avoid the use of live vaccines with ABRILADA [see Warnings and Precautions (5.10)].

7.4 Cytochrome P450 Substrates

The formation of CYP450 enzymes may be suppressed by increased concentrations of cytokines (e.g., TNFα, IL-6) during chronic inflammation. It is possible for products that antagonize cytokine activity, such as adalimumab products, to influence the formation of CYP450 enzymes. Upon initiation or discontinuation of ABRILADA in patients being treated with CYP450 substrates with a narrow therapeutic index, monitoring of the effect (e.g., warfarin) or drug concentration (e.g., cyclosporine or theophylline) is recommended and the individual dose of the drug product may be adjusted as needed.

8 USE IN SPECIFIC POPULATIONS

8.1 Pregnancy

Risk Summary

Available studies with use of adalimumab during pregnancy do not reliably establish an association between adalimumab and major birth defects. Clinical data are available from the Organization of Teratology Information Specialists (OTIS)/MotherToBaby Pregnancy Registry in pregnant women with rheumatoid arthritis (RA) or Crohn's disease (CD) treated with adalimumab. Registry results showed a rate of 10% for major birth defects with first trimester use of adalimumab in pregnant women with RA or CD and a rate of 7.5% for major birth defects in the disease-matched comparison cohort. The lack of pattern of major birth defects is reassuring and differences between exposure groups may have impacted the occurrence of birth defects (see Data).

Adalimumab is actively transferred across the placenta during the third trimester of pregnancy and may affect immune response in the in utero exposed infant (see Clinical Considerations). In an embryo-fetal perinatal development study conducted in cynomolgus monkeys, no fetal harm or malformations were observed with intravenous administration of adalimumab during organogenesis and later in gestation, at doses that produced exposures up to approximately 373 times the maximum recommended human dose (MRHD) of 40 mg subcutaneous without methotrexate (see Data).

The estimated background risk of major birth defects and miscarriage for the indicated populations is unknown. All pregnancies have a background risk of birth defect, loss, or other adverse outcomes. In the U.S. general population, the estimated background risk of major birth defects and miscarriage in clinically recognized pregnancies is 2–4% and 15–20%, respectively.

Clinical Considerations

Disease-Associated Maternal and Embryo/Fetal Risk

Published data suggest that the risk of adverse pregnancy outcomes in women with RA or inflammatory bowel disease (IBD) is associated with increased disease activity. Adverse pregnancy outcomes include preterm delivery (before 37 weeks of gestation), low birth weight (less than 2500 g) infants, and small for gestational age at birth.

Fetal/Neonatal Adverse Reactions

Monoclonal antibodies are increasingly transported across the placenta as pregnancy progresses, with the largest amount transferred during the third trimester (see Data). Risks and benefits should be considered prior to administering live or live-attenuated vaccines to infants exposed to adalimumab products in utero [see Use in Specific Populations (8.4)].

Data

Human Data

A prospective cohort pregnancy exposure registry conducted by OTIS/MotherToBaby in the U.S. and Canada between 2004 and 2016 compared the risk of major birth defects in live-born infants of 221 women (69 RA, 152 CD) treated with adalimumab during the first trimester and 106 women (74 RA, 32 CD) not treated with adalimumab.

The proportion of major birth defects among live-born infants in the adalimumab-treated and untreated cohorts was 10% (8.7% RA, 10.5% CD) and 7.5% (6.8% RA, 9.4% CD), respectively. The lack of pattern of major birth defects is reassuring and differences between exposure groups may have impacted the occurrence of birth defects. This study cannot reliably establish whether there is an association between adalimumab and major birth defects because of methodological limitations of the registry, including small sample size, the voluntary nature of the study, and the non-randomized design.

In an independent clinical study conducted in ten pregnant women with IBD treated with adalimumab, adalimumab concentrations were measured in maternal serum as well as in cord blood (n=10) and infant serum (n=8) on the day of birth. The last dose of adalimumab was given between 1 and 56 days prior to delivery. Adalimumab concentrations were 0.16–19.7 mcg/mL in cord blood, 4.28–17.7 mcg/mL in infant serum, and 0–16.1 mcg/mL in maternal serum. In all but one case, the cord blood concentration of adalimumab was higher than the maternal serum concentration, suggesting adalimumab actively crosses the placenta. In addition, one infant had serum concentrations at each of the following: 6 weeks (1.94 mcg/mL), 7 weeks (1.31 mcg/mL), 8 weeks (0.93 mcg/mL), and 11 weeks (0.53 mcg/mL), suggesting adalimumab can be detected in the serum of infants exposed in utero for at least 3 months from birth.

Animal Data

In an embryo-fetal perinatal development study, pregnant cynomolgus monkeys received adalimumab from gestation days 20 to 97 at doses that produced exposures up to 373 times that achieved with the MRHD without methotrexate (on an AUC basis with maternal IV doses up to 100 mg/kg/week). Adalimumab did not elicit harm to the fetuses or malformations.

8.2 Lactation

Risk Summary

Limited data from case reports in the published literature describe the presence of adalimumab in human milk at infant doses of 0.1% to 1% of the maternal serum concentration. Published data suggest that the systemic exposure to a breastfed infant is expected to be low because adalimumab is a large molecule and is degraded in the gastrointestinal tract. However, the effects of local exposure in the gastrointestinal tract are unknown. There are no reports of adverse effects of adalimumab products on the breastfed infant and no effects on milk production. The developmental and health benefits of breastfeeding should be considered along with the mother's clinical need for ABRILADA and any potential adverse effects on the breastfed child from ABRILADA or from the underlying maternal condition.

8.4 Pediatric Use

The safety and effectiveness of ABRILADA have not been established in pediatric patients with psoriatic arthritis, ankylosing spondylitis, or plaque psoriasis.

The safety and effectiveness of ABRILADA have been established for:

- reducing signs and symptoms of moderately to severely active polyarticular JIA in pediatric patients 2 years of age and older.
- the treatment of moderately to severely active Crohn's disease in pediatric patients 6 years of age and older.

Pediatric assessments for ABRILADA demonstrate that ABRILADA is safe and effective for pediatric patients in indications for which Humira (adalimumab) is approved. However, ABRILADA is not approved for such indications due to marketing exclusivity for Humira (adalimumab).

Due to their inhibition of TNFα, adalimumab products administered during pregnancy could affect immune response in the in utero-exposed newborn and infant. Data from eight infants exposed to adalimumab in utero suggest adalimumab crosses the placenta [see Use in Specific Populations (8.1)]. The clinical significance of elevated adalimumab concentrations in infants is unknown. The safety of administering live or live-attenuated vaccines in exposed infants is unknown. Risks and benefits should be considered prior to vaccinating (live or live-attenuated) exposed infants.

Postmarketing cases of lymphoma, including hepatosplenic T-cell lymphoma and other malignancies, some fatal, have been reported among children, adolescents, and young adults who received treatment with TNF-blockers including adalimumab products [see Warnings and Precautions (5.2)].

Juvenile Idiopathic Arthritis

The safety and effectiveness of ABRILADA for the treatment of moderately to severely active polyarticular JIA have been established in pediatric patients 2 years of age and older. Use for this indication is supported by evidence from an adequate and well-controlled study (Study JIA) of adalimumab in patients 4 to 17 years of age [see Clinical Studies (14.2)] and a safety study (Study JIA-II) of adalimumab in patients 2 to <4 years of age where the safety profile was similar to patients 4 to 17 years of age [see Adverse Reactions (6.1)]. Adalimumab products have not been studied in patients with polyarticular JIA less than 2 years of age or in patients with a weight below 10 kg.

The safety of adalimumab in pediatric patients in the polyarticular JIA trials was generally similar to that observed in adults with certain exceptions [see Adverse Reactions (6.1)].

The safety and effectiveness of ABRILADA have not been established in pediatric patients with JIA less than 2 years of age.

Pediatric Crohn's Disease

The safety and effectiveness of ABRILADA for the treatment of moderately to severely active Crohn's disease have been established in pediatric patients 6 years of age and older. Use of ABRILADA for this indication is supported by evidence from adequate and well-controlled studies in adults with additional data from a randomized, double-blind, 52-week clinical study of two dose concentrations of adalimumab in 192 pediatric patients (6 years to 17 years of age) [see Adverse Reactions (6.1), Clinical Pharmacology (12.2, 12.3), Clinical Studies (14.6)]. The adverse reaction profile in patients 6 years to 17 years of age was similar to adults.

The safety and effectiveness of ABRILADA have not been established in pediatric patients with Crohn's disease less than 6 years of age.

8.5 Geriatric Use

In clinical studies of RA (Studies RA-I, RA-II, RA-III, and RA-IV), a total of 519 subjects 65 years of age and older, including 107 subjects 75 years of age and older, received adalimumab. No overall difference in effectiveness was observed between these subjects and younger adult subjects. The frequency of serious infection and malignancy among adalimumab‑treated subjects 65 years of age and older was higher than for those less than 65 years of age. Consider the benefits and risks of ABRILADA in patients 65 years of age and older. In patients treated with ABRILADA, closely monitor for the development of infection or malignancy [see Warnings and Precautions (5.1, 5.2)].

10 OVERDOSAGE

Doses up to 10 mg/kg have been administered to patients in clinical trials without evidence of dose-limiting toxicities. In case of overdosage, it is recommended that the patient be monitored for any signs or symptoms of adverse reactions or effects and appropriate symptomatic treatment instituted immediately.

Consider contacting the Poison Help line (1-800-222-1222) or medical toxicologist for additional overdose management recommendations.

11 DESCRIPTION

Adalimumab-afzb is a tumor necrosis factor (TNF) blocker. Adalimumab-afzb is a recombinant human IgG1 monoclonal antibody with human derived heavy and light chain variable regions and human IgG1:k constant regions. Adalimumab-afzb is produced by recombinant DNA technology in Chinese hamster ovary cells and is purified by a process that includes specific viral inactivation and removal steps. It consists of 1330 amino acids and has a molecular weight of approximately 148 kilodaltons.

ABRILADA (adalimumab-afzb) injection is supplied as a sterile, preservative-free solution for subcutaneous administration. The drug product is supplied as either a single-dose prefilled pen (ABRILADA pen), as a single-dose 1 mL prefilled glass syringe, or as a single-dose institutional use vial. Enclosed within the pen is a single-dose 1 mL prefilled glass syringe. The solution of ABRILADA is clear and colorless to very light brown, with a pH of about 5.5.

Each 40 mg/0.8 mL prefilled syringe, prefilled pen, or single-dose institutional use vial delivers 0.8 mL (40 mg) of drug product. Each 0.8 mL of ABRILADA contains adalimumab-afzb (40 mg), edetate disodium dihydrate (0.04 mg), L-histidine (0.63mg), L-histidine hydrochloride monohydrate (2.51 mg), L-methionine (0.16 mg), polysorbate 80 (0.16 mg), sucrose (68 mg), and Water for Injection, USP.

Each 20 mg/0.4 mL prefilled syringe delivers 0.4 mL (20 mg) of drug product. Each 0.4 mL of ABRILADA contains adalimumab-afzb (20 mg), edetate disodium dihydrate (0.02 mg), L-histidine (0.314 mg), L-histidine hydrochloride monohydrate (1.253 mg), L-methionine (0.08 mg), polysorbate 80 (0.08 mg), sucrose (34 mg), and Water for Injection, USP.

Each 10 mg/0.2 mL prefilled syringe delivers 0.2 mL (10 mg) of drug product. Each 0.2 mL of ABRILADA contains adalimumab-afzb (10 mg), edetate disodium dihydrate (0.01 mg), L-histidine (0.157 mg), L-histidine hydrochloride monohydrate (0.626 mg), L-methionine (0.04 mg), polysorbate 80 (0.04 mg), sucrose (17 mg), and Water for Injection, USP.

12 CLINICAL PHARMACOLOGY

12.1 Mechanism of Action

Adalimumab products bind specifically to TNF-alpha and block its interaction with the p55 and p75 cell surface TNF receptors. Adalimumab products also lyse surface TNF expressing cells in vitro in the presence of complement. Adalimumab products do not bind or inactivate lymphotoxin (TNF-beta). TNF is a naturally occurring cytokine that is involved in normal inflammatory and immune responses. Elevated concentrations of TNF are found in the synovial fluid of patients with RA, JIA, PsA, and AS and play an important role in both the pathologic inflammation and the joint destruction that are hallmarks of these diseases. Increased concentrations of TNF are also found in psoriasis plaques. In Ps, treatment with ABRILADA may reduce the epidermal thickness and infiltration of inflammatory cells. The relationship between these pharmacodynamic activities and the mechanism(s) by which adalimumab products exert their clinical effects is unknown.

Adalimumab products also modulate biological responses that are induced or regulated by TNF, including changes in the concentrations of adhesion molecules responsible for leukocyte migration (ELAM-1, VCAM-1, and ICAM-1 with an IC50 of 1–2 × 10^-10M).

12.2 Pharmacodynamics

After treatment with adalimumab, a decrease in concentrations of acute phase reactants of inflammation (C-reactive protein [CRP] and erythrocyte sedimentation rate [ESR]) and serum cytokines (IL-6) was observed compared to baseline in patients with rheumatoid arthritis. A decrease in CRP concentrations was also observed in patients with Crohn's disease, ulcerative colitis, and hidradenitis suppurativa. Serum concentrations of matrix metalloproteinases (MMP-1 and MMP-3) that produce tissue remodeling responsible for cartilage destruction were also decreased after adalimumab administration.

12.3 Pharmacokinetics

The pharmacokinetics of adalimumab were linear over the dose range of 0.5 to 10 mg/kg following administration of a single intravenous dose (adalimumab products are not approved for intravenous use). Following 20, 40, and 80 mg every other week and every week subcutaneous administration, adalimumab mean serum trough concentrations at steady state increased approximately proportionally with dose in RA patients. The mean terminal half-life was approximately 2 weeks, ranging from 10 to 20 days across studies. Healthy subjects and patients with RA displayed similar adalimumab pharmacokinetics.

Adalimumab exposure in patients treated with 80 mg every other week is estimated to be comparable with that in patients treated with 40 mg every week.

Absorption

The average absolute bioavailability of adalimumab following a single 40 mg subcutaneous dose was 64%. The mean time to reach the maximum concentration was 5.5 days (131 ± 56 hours) and the maximum serum concentration was 4.7 ± 1.6 mcg/mL in healthy subjects following a single 40 mg subcutaneous administration of adalimumab.

Distribution

The distribution volume (Vss) ranged from 4.7 to 6.0 L following intravenous administration of doses ranging from 0.25 to 10 mg/kg in RA patients.

Elimination

The single-dose pharmacokinetics of adalimumab in RA patients were determined in several studies with intravenous doses ranging from 0.25 to 10 mg/kg. The systemic clearance of adalimumab is approximately 12 mL/hr. In long-term studies with dosing more than two years, there was no evidence of changes in clearance over time in RA patients.

Patient Population

Rheumatoid Arthritis and Ankylosing Spondylitis: In patients receiving 40 mg adalimumab every other week, adalimumab mean steady-state trough concentrations were approximately 5 mcg/mL and 8 to 9 mcg/mL, without and with MTX concomitant treatment, respectively. Adalimumab concentrations in the synovial fluid from five rheumatoid arthritis patients ranged from 31 to 96% of those in serum. The pharmacokinetics of adalimumab in patients with AS were similar to those in patients with RA.

Psoriatic Arthritis: In patients receiving 40 mg every other week, adalimumab mean steady-state trough concentrations were 6 to 10 mcg/mL and 8.5 to 12 mcg/mL, without and with MTX concomitant treatment, respectively.

Plaque Psoriasis: Adalimumab mean steady-state trough concentration was approximately 5 to 6 mcg/mL during adalimumab 40 mg every other week treatment.

Adult Uveitis: Adalimumab mean steady concentration was approximately 8 to 10 mcg/mL during adalimumab 40 mg every other week treatment.

Adult Hidradenitis Suppurativa: Adalimumab trough concentrations were approximately 7 to 8 mcg/mL at Week 2 and Week 4, respectively, after receiving 160 mg on Week 0 followed by 80 mg on Week 2. Mean steady-state trough concentrations at Week 12 through Week 36 were approximately 7 to 11 mcg/mL during adalimumab 40 mg every week treatment.

Adult Crohn's Disease: Adalimumab mean trough concentrations were approximately 12 mcg/mL at Week 2 and Week 4 after receiving 160 mg on Week 0 followed by 80 mg on Week 2. Mean steady-state trough concentrations were 7 mcg/mL at Week 24 and Week 56 during adalimumab 40 mg every other week treatment.

Adult Ulcerative Colitis: Adalimumab mean trough concentrations were approximately 12 mcg/mL at Week 2 and Week 4 after receiving 160 mg on Week 0 followed by 80 mg on Week 2. Mean steady-state trough concentrations were approximately 8 mcg/mL and 15 mcg/mL at Week 52 after receiving a dose of adalimumab 40 mg every other week and 40 mg every week, respectively.

Anti-Drug Antibody Effects on Pharmacokinetics

Rheumatoid Arthritis: A trend toward higher apparent clearance of adalimumab in the presence of anti-adalimumab antibodies was identified.

Hidradenitis Suppurativa: In subjects with moderate to severe HS, antibodies to adalimumab were associated with reduced serum adalimumab concentrations. In general, the extent of reduction in serum adalimumab concentrations is greater with increasing titers of antibodies to adalimumab.

Specific Populations

Geriatric Patients: A lower clearance with increasing age was observed in patients with RA aged 40 to >75 years.

Pediatric Patients:

Juvenile Idiopathic Arthritis:

- 4 years to 17 years of age: The adalimumab mean steady-state trough concentrations were 6.8 mcg/mL and 10.9 mcg/mL in patients weighing <30 kg receiving 20 mg adalimumab subcutaneously every other week as monotherapy or with concomitant MTX, respectively. The adalimumab mean steady-state trough concentrations were 6.6 mcg/mL and 8.1 mcg/mL in patients weighing ≥30 kg receiving 40 mg adalimumab subcutaneously every other week as monotherapy or with MTX concomitant treatment, respectively.
- 2 years to <4 years of age or 4 years of age and older weighing <15 kg: The adalimumab mean steady-state trough adalimumab concentrations were 6.0 mcg/mL and 7.9 mcg/mL in patients receiving adalimumab subcutaneously every other week as monotherapy or with MTX concomitant treatment, respectively.

Pediatric Crohn's Disease: Adalimumab mean ± SD concentrations were 15.7 ± 6.5 mcg/mL at Week 4 following 160 mg at Week 0 and 80 mg at Week 2, and 10.5 ± 6.0 mcg/mL at Week 52 following 40 mg every other week dosing in patients weighing ≥40 kg. Adalimumab mean ± SD concentrations were 10.6 ± 6.1 mcg/mL at Week 4 following dosing 80 mg at Week 0 and 40 mg at Week 2, and 6.9 ± 3.6 mcg/mL at Week 52 following 20 mg every other week dosing in patients weighing <40 kg.

Male and Female Patients: No gender-related pharmacokinetic differences were observed after correction for a patient's body weight. Healthy subjects and patients with rheumatoid arthritis displayed similar adalimumab pharmacokinetics.

Patients with Renal or Hepatic Impairment: No pharmacokinetic data are available in patients with hepatic or renal impairment.

Rheumatoid Factor or CRP Concentrations: Minor increases in apparent clearance were predicted in RA patients receiving doses lower than the recommended dose and in RA patients with high rheumatoid factor or CRP concentrations. These increases are not likely to be clinically important.

Drug Interaction Studies:

Methotrexate: MTX reduced adalimumab apparent clearance after single and multiple dosing by 29% and 44% respectively, in patients with RA [see Drug Interactions (7.1)].

13 NONCLINICAL TOXICOLOGY

13.1 Carcinogenesis, Mutagenesis, Impairment of Fertility

Long-term animal studies of adalimumab products have not been conducted to evaluate the carcinogenic potential or its effect on fertility.

14 CLINICAL STUDIES

14.1 Clinical Studies in Rheumatoid Arthritis

The efficacy and safety of adalimumab were assessed in five randomized, double‑blind studies in subjects ≥18 years of age with active rheumatoid arthritis (RA) diagnosed according to American College of Rheumatology (ACR) criteria. Subjects had at least 6 swollen and 9 tender joints.

Adalimumab was administered subcutaneously in combination with methotrexate (MTX) (12.5 to 25 mg, Studies RA-I, RA-III and RA-V) or as monotherapy (Studies RA-II and RA-V) or with other disease-modifying anti-rheumatic drugs (DMARDs) (Study RA-IV).

Study RA-I evaluated 271 subjects who had failed therapy with at least one but no more than four DMARDs and had inadequate response to MTX. Doses of 20, 40 or 80 mg of adalimumab or placebo were given every other week for 24 weeks.

Study RA-II evaluated 544 subjects who had failed therapy with at least one DMARD. Doses of placebo, 20 or 40 mg of adalimumab were given as monotherapy every other week or weekly for 26 weeks.

Study RA-III evaluated 619 subjects who had an inadequate response to MTX. Subjects received placebo, 40 mg of adalimumab every other week with placebo injections on alternate weeks, or 20 mg of adalimumab weekly for up to 52 weeks. Study RA-III had an additional primary endpoint at 52 weeks of inhibition of disease progression (as detected by X-ray results). Upon completion of the first 52 weeks, 457 subjects enrolled in an open-label extension phase in which 40 mg of adalimumab was administered every other week for up to 5 years.

Study RA-IV assessed safety in 636 subjects who were either DMARD-naive or were permitted to remain on their pre-existing rheumatologic therapy provided that therapy was stable for a minimum of 28 days. Subjects were randomized to 40 mg of adalimumab or placebo every other week for 24 weeks.

Study RA-V evaluated 799 subjects with moderately to severely active RA of less than 3 years duration who were ≥18 years old and MTX naïve. Subjects were randomized to receive either MTX (optimized to 20 mg/week by Week 8), adalimumab 40 mg every other week or adalimumab/MTX combination therapy for 104 weeks. Subjects were evaluated for signs and symptoms, and for radiographic progression of joint damage. The median disease duration among subjects enrolled in the study was 5 months. The median MTX dose achieved was 20 mg.

Clinical Response

The percent of adalimumab-treated subjects achieving ACR 20, 50, and 70 responses in Studies RA-II and III are shown in Table 3.

Table 3. ACR Responses in Studies RA-II and RA-III (Percent of Subjects)
Response | Study RA-II Monotherapy (26 weeks) |  |  | Study RA-III Methotrexate Combination (24 and 52 weeks)
Response | Placebo N=110 | Adalimumab 40 mg Every Other Week N=113 | Adalimumab 40 mg Weekly N=103 | Placebo/MTX N=200 | Adalimumab/MTX 40 mg Every Other Week N=207
ACR20
Month 6 | 19% | 46% [p<0.01, adalimumab vs. placebo.] | 53% | 30% | 63%
Month 12 | NA | NA | NA | 24% | 59%
ACR50
Month 6 | 8% | 22% | 35% | 10% | 39%
Month 12 | NA | NA | NA | 10% | 42%
ACR70
Month 6 | 2% | 12% | 18% | 3% | 21%
Month 12 | NA | NA | NA | 5% | 23%

The results of Study RA-I were similar to Study RA-III; subjects receiving adalimumab 40 mg every other week in Study RA-I also achieved ACR 20, 50, and 70 response rates of 65%, 52%, and 24%, respectively, compared to placebo responses of 13%, 7%, and 3% respectively, at 6 months (p<0.01).

The results of the components of the ACR response criteria for Studies RA-II and RA-III are shown in Table 4. ACR response rates and improvement in all components of ACR response were maintained to Week 104. Over the 2 years in Study RA-III, 20% of adalimumab subjects receiving 40 mg every other week achieved a major clinical response, defined as maintenance of an ACR 70 response over a 6-month period. ACR responses were maintained in similar proportions of subjects for up to 5 years with continuous adalimumab treatment in the open-label portion of Study RA-III.

Table 4. Components of ACR Response in Studies RA-II and RA-III
Parameter (median) | Study RA-II |  |  |  | Study RA-III
Parameter (median) | Placebo N=110 |  | Adalimumab [40 mg adalimumab administered every other week.] N=113 |  | Placebo/MTX N=200 |  | Adalimumab/MTX N=207
Parameter (median) | Baseline | Wk 26 | Baseline | Wk 26 | Baseline | Wk 24 | Baseline | Wk 24
Number of tender joints (0–68) | 35 | 26 | 31 | 16 [p<0.001, adalimumab vs. placebo, based on mean change from baseline.] | 26 | 15 | 24 | 8
Number of swollen joints (0–66) | 19 | 16 | 18 | 10 | 17 | 11 | 18 | 5
Physician global assessment [Visual analogue scale; 0=best, 10=worst.] | 7.0 | 6.1 | 6.6 | 3.7 | 6.3 | 3.5 | 6.5 | 2.0
Patient global assessment | 7.5 | 6.3 | 7.5 | 4.5 | 5.4 | 3.9 | 5.2 | 2.0
Pain | 7.3 | 6.1 | 7.3 | 4.1 | 6.0 | 3.8 | 5.8 | 2.1
Disability index (HAQ) [Disability Index of the Health Assessment Questionnaire; 0=best, 3=worst, measures the patient's ability to perform the following: dress/groom, arise, eat, walk, reach, grip, maintain hygiene, and maintain daily activity.] | 2.0 | 1.9 | 1.9 | 1.5 | 1.5 | 1.3 | 1.5 | 0.8
CRP (mg/dL) | 3.9 | 4.3 | 4.6 | 1.8 | 1.0 | 0.9 | 1.0 | 0.4

The time course of ACR 20 response for Study RA-III is shown in Figure 1.

In Study RA-III, 85% of subjects with ACR 20 responses at Week 24 maintained the response at 52 weeks. The time course of ACR 20 response for Study RA-I and Study RA-II were similar.

Figure 1. Study RA-III ACR 20 Responses Over 52 Weeks

In Study RA-IV, 53% of subjects treated with adalimumab 40 mg every other week plus standard of care had an ACR 20 response at Week 24 compared to 35% on placebo plus standard of care (p<0.001). No unique adverse reactions related to the combination of adalimumab and other DMARDs were observed.

In Study RA-V with MTX naïve subjects with recent onset RA, the combination treatment with adalimumab plus MTX led to greater percentages of subjects achieving ACR responses than either MTX monotherapy or adalimumab monotherapy at Week 52 and responses were sustained at Week 104 (see Table 5).

Table 5. ACR Response in Study RA-V (Percent of Subjects)
Response | MTX [p<0.05, adalimumab/MTX vs. MTX for ACR 20; p<0.001, adalimumab/MTX vs. MTX for ACR 50 and 70, and Major Clinical Response.] N=257 | Adalimumab [p<0.001, adalimumab/MTX vs. adalimumab.] N=274 | Adalimumab/MTX N=268
ACR20
Week 52 | 63% | 54% | 73%
Week 104 | 56% | 49% | 69%
ACR50
Week 52 | 46% | 41% | 62%
Week 104 | 43% | 37% | 59%
ACR70
Week 52 | 27% | 26% | 46%
Week 104 | 28% | 28% | 47%
Major Clinical Response [Major clinical response is defined as achieving an ACR70 response for a continuous six month period.] | 28% | 25% | 49%

At Week 52, all individual components of the ACR response criteria for Study RA-V improved in the adalimumab/MTX group and improvements were maintained to Week 104.

Radiographic Response

In Study RA-III, structural joint damage was assessed radiographically and expressed as change in Total Sharp Score (TSS) and its components, the erosion score and Joint Space Narrowing (JSN) score, at Month 12 compared to baseline. At baseline, the median TSS was approximately 55 in the placebo and 40 mg every other week groups. The results are shown in Table 6. Adalimumab/MTX treated subjects demonstrated less radiographic progression than subjects receiving MTX alone at 52 weeks.

Table 6. Radiographic Mean Changes Over 12 Months in Study RA-III
 | Placebo/MTX | Adalimumab/MTX 40 mg Every Other Week | Placebo/MTX Adalimumab/MTX (95% Confidence Interval [95% confidence intervals for the differences in change scores between MTX and adalimumab.]) | P-value [Based on rank analysis.]
Total Sharp score | 2.7 | 0.1 | 2.6 (1.4, 3.8) | <0.001
Erosion score | 1.6 | 0.0 | 1.6 (0.9, 2.2) | <0.001
JSN score | 1.0 | 0.1 | 0.9 (0.3, 1.4) | 0.002

In the open-label extension of Study RA-III, 77% of the original subjects treated with any dose of adalimumab were evaluated radiographically at 2 years. Subjects maintained inhibition of structural damage, as measured by the TSS. Fifty-four percent had no progression of structural damage as defined by a change in the TSS of zero or less. Fifty-five percent (55%) of subjects originally treated with 40 mg adalimumab every other week have been evaluated radiographically at 5 years. Subjects had continued inhibition of structural damage with 50% showing no progression of structural damage defined by a change in the TSS of zero or less.

In Study RA-V, structural joint damage was assessed as in Study RA-III. Greater inhibition of radiographic progression, as assessed by changes in TSS, erosion score and JSN was observed in the adalimumab/MTX combination group as compared to either the MTX or adalimumab monotherapy group at Week 52 as well as at Week 104 (see Table 7).

Table 7. Radiographic Mean Change [mean (95% confidence interval).] in Study RA-V
 |  | MTX [p<0.001, adalimumab/MTX vs. MTX at 52 and 104 weeks and for adalimumab/MTX vs. adalimumab at 104 weeks.] N=257 | Adalimumab, [p<0.01, for adalimumab/MTX vs. adalimumab at 52 weeks.] N=274 | Adalimumab/MTX N=268
52 Weeks | Total Sharp score | 5.7 (4.2, 7.3) | 3.0 (1.7, 4.3) | 1.3 (0.5, 2.1)
 | Erosion score | 3.7 (2.7, 4.8) | 1.7 (1.0, 2.4) | 0.8 (0.4, 1.2)
 | JSN score | 2.0 (1.2, 2.8) | 1.3 (0.5, 2.1) | 0.5 (0.0, 1.0)
104 Weeks | Total Sharp score | 10.4 (7.7, 13.2) | 5.5 (3.6, 7.4) | 1.9 (0.9, 2.9)
 | Erosion score | 6.4 (4.6, 8.2) | 3.0 (2.0, 4.0) | 1.0 (0.4, 1.6)
 | JSN score | 4.1 (2.7, 5.4) | 2.6 (1.5, 3.7) | 0.9 (0.3, 1.5)

Physical Function Response

In Studies RA-I through IV, adalimumab showed significantly greater improvement than placebo in the disability index of Health Assessment Questionnaire (HAQ-DI) from baseline to the end of study, and significantly greater improvement than placebo in the health-outcomes as assessed by the Short Form Health Survey (SF 36). Improvement was seen in both the Physical Component Summary (PCS) and the Mental Component Summary (MCS).

In Study RA‑III, the mean (95% CI) improvement in HAQ‑DI from baseline at Week 52 was 0.60 (0.55, 0.65) for the adalimumab subjects and 0.25 (0.17, 0.33) for placebo/MTX (p<0.001) subjects. Sixty‑three percent of adalimumab‑treated subjects achieved a 0.5 or greater improvement in HAQ‑DI at Week 52 in the double‑blind portion of the study. Eighty‑two percent of these subjects maintained that improvement through Week 104 and a similar proportion of subjects maintained this response through Week 260 (5 years) of open‑label treatment. Mean improvement in the SF‑36 was maintained through the end of measurement at Week 156 (3 years).

In Study RA-V, the HAQ-DI and the physical component of the SF-36 showed greater improvement (p<0.001) for the adalimumab/MTX combination therapy group versus either the MTX monotherapy or the adalimumab monotherapy group at Week 52, which was maintained through Week 104.

14.2 Clinical Studies in Juvenile Idiopathic Arthritis

The safety and efficacy of adalimumab were assessed in two studies (Studies JIA-I and JIA-II) in subjects with active polyarticular juvenile idiopathic arthritis (JIA).

Study JIA-I

The safety and efficacy of adalimumab were assessed in a multicenter, randomized, withdrawal, double‑blind, parallel‑group study in 171 subjects who were 4 to 17 years of age with polyarticular JIA. In the study, the subjects were stratified into two groups: MTX‑treated or non MTX‑treated. All subjects had to show signs of active moderate or severe disease despite previous treatment with NSAIDs, analgesics, corticosteroids, or DMARDs. Subjects who received prior treatment with any biologic DMARDs were excluded from the study.

The study included four phases: an open‑label lead in phase (OL‑LI; 16 weeks), a double‑blind randomized withdrawal phase (DB; 32 weeks), an open‑label extension phase (OLE‑BSA; up to 136 weeks), and an open‑label fixed dose phase (OLE‑FD; 16 weeks). In the first three phases of the study, adalimumab was administered based on body surface area at a dose of 24 mg/m^2 up to a maximum total body dose of 40 mg subcutaneously (SC) every other week. In the OLE‑FD phase, the subjects were treated with 20 mg of adalimumab SC every other week if their weight was less than 30 kg and with 40 mg of adalimumab SC every other week if their weight was 30 kg or greater. Subjects remained on stable doses of NSAIDs and or prednisone (≤0.2 mg/kg/day or 10 mg/day maximum).

Subjects demonstrating a Pediatric ACR 30 response at the end of OL‑LI phase were randomized into the double‑blind (DB) phase of the study and received either adalimumab or placebo every other week for 32 weeks or until disease flare. Disease flare was defined as a worsening of ≥30% from baseline in ≥3 of 6 Pediatric ACR core criteria, ≥2 active joints, and improvement of >30% in no more than 1 of the 6 criteria. After 32 weeks or at the time of disease flare during the DB phase, subjects were treated in the open‑label extension phase based on the BSA regimen (OLE‑BSA), before converting to a fixed dose regimen based on body weight (OLE‑FD phase).

Study JIA-I Clinical Response

At the end of the 16‑week OL‑LI phase, 94% of the subjects in the MTX stratum and 74% of the subjects in the non‑MTX stratum were Pediatric ACR 30 responders. In the DB phase significantly fewer subjects who received adalimumab experienced disease flare compared to placebo, both without MTX (43% vs. 71%) and with MTX (37% vs. 65%). More subjects treated with adalimumab continued to show pediatric ACR 30/50/70 responses at Week 48 compared to subjects treated with placebo. Pediatric ACR responses were maintained for up to two years in the OLE phase in subjects who received adalimumab throughout the study.

Study JIA-II

Adalimumab was assessed in an open-label, multicenter study in 32 subjects who were 2 to <4 years of age or 4 years of age and older weighing <15 kg with moderately to severely active polyarticular JIA. Most subjects (97%) received at least 24 weeks of adalimumab treatment dosed 24 mg/m^2 up to a maximum of 20 mg every other week as a single SC injection up to a maximum of 120 weeks duration. During the study, most subjects used concomitant MTX, with fewer reporting use of corticosteroids or NSAIDs. The primary objective of the study was evaluation of safety [see Adverse Reactions (6.1)].

14.3 Clinical Studies in Psoriatic Arthritis

The safety and efficacy of adalimumab were assessed in two randomized, double‑blind, placebo‑controlled studies in 413 subjects with psoriatic arthritis (PsA). Upon completion of both studies, 383 subjects enrolled in an open‑label extension study, in which 40 mg adalimumab was administered every other week.

Study PsA‑I enrolled 313 adult subjects with moderately to severely active PsA (>3 swollen and >3 tender joints) who had an inadequate response to NSAID therapy in one of the following forms: (1) distal interphalangeal (DIP) involvement (N=23); (2) polyarticular arthritis (absence of rheumatoid nodules and presence of plaque psoriasis) (N=210); (3) arthritis mutilans (N=1); (4) asymmetric PsA (N=77); or (5) AS‑like (N=2). Subjects on MTX therapy (158 of 313 subjects) at enrollment (stable dose of ≤30 mg/week for >1 month) could continue MTX at the same dose. Doses of adalimumab 40 mg or placebo every other week were administered during the 24‑week double‑blind period of the study.

Compared to placebo, treatment with adalimumab resulted in improvements in the measures of disease activity (see Tables 8 and 9). Among subjects with PsA who received adalimumab, the clinical responses were apparent in some subjects at the time of the first visit (two weeks) and were maintained up to 88 weeks in the ongoing open‑label study. Similar responses were seen in subjects with each of the subtypes of psoriatic arthritis, although few subjects were enrolled with the arthritis mutilans and ankylosing spondylitis‑like subtypes. Responses were similar in subjects who were or were not receiving concomitant MTX therapy at baseline.

Subjects with psoriatic involvement of at least three percent body surface area (BSA) were evaluated for Psoriatic Area and Severity Index (PASI) responses. At 24 weeks, the proportions of subjects achieving a 75% or 90% improvement in the PASI were 59% and 42% respectively, in the adalimumab group (N=69), compared to 1% and 0% respectively, in the placebo group (N=69) (p<0.001). PASI responses were apparent in some subjects at the time of the first visit (two weeks). Responses were similar in subjects who were or were not receiving concomitant MTX therapy at baseline.

Table 8. ACR Response in Study PsA-I (Percent of Subjects)
 | Placebo N=162 | Adalimumab [p<0.001 for all comparisons between adalimumab and placebo.] N=151
ACR20
Week 12; Week 24 | 14%; 15% | 58%; 57%
ACR50
Week 12; Week 24 | 4%; 6% | 36%; 39%
ACR70
Week 12; Week 24 | 1%; 1% | 20%; 23%

Table 9. Components of Disease Activity in Study PsA-I
 | Placebo N=162 |  | Adalimumab [p<0.001 for adalimumab vs. placebo comparisons based on median changes.] N=151
Parameter: median | Baseline | 24 weeks | Baseline | 24 weeks
Number of tender joints [Scale 0–78.] | 23.0 | 17.0 | 20.0 | 5.0
Number of swollen joints [Scale 0–76.] | 11.0 | 9.0 | 11.0 | 3.0
Physician global assessment [Visual analog scale; 0=best, 100=worst.] | 53.0 | 49.0 | 55.0 | 16.0
Patient global assessment | 49.5 | 49.0 | 48.0 | 20.0
Pain | 49.0 | 49.0 | 54.0 | 20.0
Disability index (HAQ) [Disability Index of the Health Assessment Questionnaire; 0=best, 3=worst; measures the patient's ability to perform the following: dress/groom, arise, eat, walk, reach, grip, maintain hygiene, and maintain daily activity.] | 1.0 | 0.9 | 1.0 | 0.4
CRP (mg/dL) [Normal range: 0–0.287 mg/dL.] | 0.8 | 0.7 | 0.8 | 0.2

Similar results were seen in an additional, 12-week study in 100 subjects with moderate to severe psoriatic arthritis who had suboptimal response to DMARD therapy as manifested by ≥3 tender joints and ≥3 swollen joints at enrollment.

Radiographic Response

Radiographic changes were assessed in the PsA studies. Radiographs of hands, wrists, and feet were obtained at baseline and Week 24 during the double‑blind period when subjects were on adalimumab or placebo and at Week 48 when all subjects were on open‑label adalimumab. A modified Total Sharp Score (mTSS), which included distal interphalangeal joints (i.e., not identical to the TSS used for rheumatoid arthritis), was used by readers blinded to treatment group to assess the radiographs.

Adalimumab‑treated subjects demonstrated greater inhibition of radiographic progression compared to placebo‑treated subjects and this effect was maintained at 48 weeks (see Table 10).

Table 10. Change in Modified Total Sharp Score in Psoriatic Arthritis
 | Placebo N=141 | Adalimumab N=133
 | Week 24 | Week 24 | Week 48
Baseline mean | 22.1 | 23.4 | 23.4
Mean change ± SD | 0.9 ± 3.1 | -0.1 ± 1.7 | -0.2 ± 4.9 [<0.001 for the difference between adalimumab, Week 48 and Placebo, Week 24 (primary analysis).]

Physical Function Response

In Study PsA‑I, physical function and disability were assessed using the HAQ Disability Index (HAQ‑DI) and the SF‑36 Health Survey. Subjects treated with 40 mg of adalimumab every other week showed greater improvement from baseline in the HAQ‑DI score (mean decreases of 47% and 49% at Weeks 12 and 24, respectively) in comparison to placebo (mean decreases of 1% and 3% at Weeks 12 and 24, respectively). At Weeks 12 and 24, subjects treated with adalimumab showed greater improvement from baseline in the SF‑36 Physical Component Summary score compared to subjects treated with placebo, and no worsening in the SF‑36 Mental Component Summary score. Improvement in physical function based on the HAQ‑DI was maintained for up to 84 weeks through the open‑label portion of the study.

14.4 Clinical Studies in Ankylosing Spondylitis

The safety and efficacy of adalimumab 40 mg every other week were assessed in 315 adult subjects in a randomized, 24 week double‑blind, placebo‑controlled study in subjects with active ankylosing spondylitis (AS) who had an inadequate response to glucocorticoids, NSAIDs, analgesics, methotrexate or sulfasalazine. Active AS was defined as subjects who fulfilled at least two of the following three criteria: (1) a Bath AS disease activity index (BASDAI) score ≥4 cm, (2) a visual analog score (VAS) for total back pain ≥40 mm, and (3) morning stiffness ≥1 hour. The blinded period was followed by an open‑label period during which subjects received adalimumab 40 mg every other week subcutaneously for up to an additional 28 weeks.

Improvement in measures of disease activity was first observed at Week 2 and maintained through 24 weeks as shown in Figure 2 and Table 11.

Responses of subjects with total spinal ankylosis (n=11) were similar to those without total ankylosis.

Figure 2. ASAS 20 Response By Visit, Study AS-I

At 12 weeks, the ASAS 20/50/70 responses were achieved by 58%, 38%, and 23%, respectively, of subjects receiving adalimumab, compared to 21%, 10%, and 5% respectively, of subjects receiving placebo (p<0.001). Similar responses were seen at Week 24 and were sustained in subjects receiving open‑label adalimumab for up to 52 weeks.

A greater proportion of subjects treated with adalimumab (22%) achieved a low level of disease activity at 24 weeks (defined as a value <20 [on a scale of 0 to 100 mm] in each of the four ASAS response parameters) compared to subjects treated with placebo (6%).

Table 11. Components of Ankylosing Spondylitis Disease Activity
 | Placebo N=107 |  | Adalimumab N=208
 | Baseline; mean | Week 24; mean | Baseline; mean | Week 24; mean
ASAS 20 Response Criteria [Statistically significant for comparisons between adalimumab and placebo at Week 24.]
Patient's Global Assessment of Disease Activity [Percent of subjects with at least a 20% and 10-unit improvement measured on a Visual Analog Scale (VAS) with 0=none and 100=severe.] , | 65 | 60 | 63 | 38
Total back pain | 67 | 58 | 65 | 37
Inflammation [Mean of questions 5 and 6 of BASDAI (defined in 'd').] , | 6.7 | 5.6 | 6.7 | 3.6
BASFI [Bath Ankylosing Spondylitis Functional Index.] , | 56 | 51 | 52 | 34
BASDAI [Bath Ankylosing Spondylitis Disease Activity Index.] score | 6.3 | 5.5 | 6.3 | 3.7
BASMI [Bath Ankylosing Spondylitis Metrology Index.] score | 4.2 | 4.1 | 3.8 | 3.3
Tragus to wall (cm) | 15.9 | 15.8 | 15.8 | 15.4
Lumbar flexion (cm) | 4.1 | 4.0 | 4.2 | 4.4
Cervical rotation (degrees) | 42.2 | 42.1 | 48.4 | 51.6
Lumbar side flexion (cm) | 8.9 | 9.0 | 9.7 | 11.7
Intermalleolar distance (cm) | 92.9 | 94.0 | 93.5 | 100.8
CRP [C-Reactive Protein (mg/dL).] , | 2.2 | 2.0 | 1.8 | 0.6

A second randomized, multicenter, double-blind, placebo-controlled study of 82 subjects with ankylosing spondylitis showed similar results.

Subjects treated with adalimumab achieved improvement from baseline in the Ankylosing Spondylitis Quality of Life Questionnaire (ASQoL) score (-3.6 vs. -1.1) and in the Short Form Health Survey (SF-36) Physical Component Summary (PCS) score (7.4 vs. 1.9) compared to placebo-treated subjects at Week 24.

14.5 Clinical Studies in Adults with Crohn's Disease

The safety and efficacy of multiple doses of adalimumab were assessed in adult subjects with moderately to severely active Crohn's disease, CD, (Crohn's Disease Activity Index (CDAI) ≥220 and ≤450) in randomized, double-blind, placebo-controlled studies. Concomitant stable doses of aminosalicylates, corticosteroids, and/or immunomodulatory agents were permitted, and 79% of subjects continued to receive at least one of these medications.

Induction of clinical remission (defined as CDAI <150) was evaluated in two studies. In Study CD-I, 299 TNF-blocker naïve subjects were randomized to one of four treatment groups: the placebo group received placebo at Weeks 0 and 2, the 160/80 group received 160 mg adalimumab at Week 0 and 80 mg at Week 2, the 80/40 group received 80 mg at Week 0 and 40 mg at Week 2, and the 40/20 group received 40 mg at Week 0 and 20 mg at Week 2. Clinical results were assessed at Week 4.

In the second induction study, Study CD-II, 325 subjects who had lost response to, or were intolerant to, previous infliximab therapy were randomized to receive either 160 mg adalimumab at Week 0 and 80 mg at Week 2, or placebo at Weeks 0 and 2. Clinical results were assessed at Week 4.

Maintenance of clinical remission was evaluated in Study CD‑III. In this study, 854 subjects with active disease received open‑label adalimumab, 80 mg at Week 0 and 40 mg at Week 2. Subjects were then randomized at Week 4 to 40 mg adalimumab every other week, 40 mg adalimumab every week, or placebo. The total study duration was 56 weeks. Subjects in clinical response (decrease in CDAI ≥70) at Week 4 were stratified and analyzed separately from those not in clinical response at Week 4.

Induction of Clinical Remission

A greater percentage of the subjects treated with 160/80 mg adalimumab achieved induction of clinical remission versus placebo at Week 4 regardless of whether the subjects were TNF blocker naïve (CD-I), or had lost response to or were intolerant to infliximab (CD-II) (see Table 12).

Table 12. Induction of Clinical Remission in Studies CD-I and CD-II (Percent of Subjects)
 | CD-I |  | CD-II
 | Placebo N=74 | Adalimumab 160/80 mg N=76 | Placebo N=166 | Adalimumab 160/80 mg N=159
Week 4
Clinical remission | 12% | 36% [p<0.001 for adalimumab vs. placebo pairwise comparison of proportions.] | 7% | 21%
Clinical response | 34% | 58% [p<0.01 for adalimumab vs. placebo pairwise comparison of proportions.] | 34% | 52%
Clinical remission is CDAI score <150; clinical response is decrease in CDAI of at least 70 points.

Maintenance of Clinical Remission

In Study CD‑III at Week 4, 58% (499/854) of subjects were in clinical response and were assessed in the primary analysis. At Weeks 26 and 56, greater proportions of subjects who were in clinical response at Week 4 achieved clinical remission in the adalimumab 40 mg every other week maintenance group compared to subjects in the placebo maintenance group (see Table 13). The group that received adalimumab therapy every week did not demonstrate significantly higher remission rates compared to the group that received adalimumab every other week.

Table 13. Maintenance of Clinical Remission in CD-III (Percent of Subjects)
 | Placebo N=170 | 40 mg Adalimumab Every Other Week N=172
Week 26
Clinical remission | 17% | 40% [p<0.001 for adalimumab vs. placebo pairwise comparisons of proportions]
Clinical response | 28% | 54%
Week 56
Clinical remission | 12% | 36%
Clinical response | 18% | 43%
Clinical remission is CDAI score <150; clinical response is decrease in CDAI of at least 70 points.

Of those in response at Week 4 who attained remission during the study, subjects in the adalimumab every other week group maintained remission for a longer time than subjects in the placebo maintenance group. Among subjects who were not in response by Week 12, therapy continued beyond 12 weeks did not result in significantly more responses.

14.6 Clinical Studies in Pediatric Subjects with Crohn’s Disease

A randomized, double-blind, 52-week clinical study of 2 dose concentrations of adalimumab (Study PCD-I) was conducted in 192 pediatric subjects (6 to 17 years of age) with moderately to severely active Crohn’s disease (defined as Pediatric Crohn’s Disease Activity Index (PCDAI) score >30). Enrolled subjects had over the previous two-year period an inadequate response to corticosteroids or an immunomodulator (i.e., azathioprine, 6-mercaptopurine, or methotrexate). Subjects who had previously received a TNF blocker were allowed to enroll if they had previously had loss of response or intolerance to that TNF blocker.

Subjects received open-label induction therapy at a dose based on their body weight (≥40 kg and <40 kg). Subjects weighing ≥40 kg received 160 mg (at Week 0) and 80 mg (at Week 2). Subjects weighing <40 kg received 80 mg (at Week 0) and 40 mg (at Week 2). At Week 4, subjects within each body weight category (≥40 kg and <40 kg) were randomized 1:1 to one of two maintenance dose regimens (high dose and low dose). The high dose was 40 mg every other week for subjects weighing ≥40 kg and 20 mg every other week for subjects weighing <40 kg. The low dose was 20 mg every other week for subjects weighing ≥40 kg and 10 mg every other week for subjects weighing <40 kg.

Concomitant stable dosages of corticosteroids (prednisone dosage ≤40 mg/day or equivalent) and immunomodulators (azathioprine, 6-mercaptopurine, or methotrexate) were permitted throughout the study.

At Week 12, subjects who experienced a disease flare (increase in PCDAI of ≥15 from Week 4 and absolute PCDAI >30) or who were non-responders (did not achieve a decrease in the PCDAI of ≥15 from baseline for 2 consecutive visits at least 2 weeks apart) were allowed to dose-escalate (i.e., switch from blinded every other week dosing to blinded every week dosing); subjects who dose-escalated were considered treatment failures.

At baseline, 38% of subjects were receiving corticosteroids, and 62% of subjects were receiving an immunomodulator. Forty-four percent (44%) of subjects had previously lost response or were intolerant to a TNF blocker. The median baseline PCDAI score was 40.

Of the 192 subjects total, 188 subjects completed the 4 week induction period, 152 subjects completed 26 weeks of treatment, and 124 subjects completed 52 weeks of treatment. Fifty-one percent (51%) (48/95) of subjects in the low maintenance dose group dose-escalated, and 38% (35/93) of subjects in the high maintenance dose group dose-escalated.

At Week 4, 28% (52/188) of subjects were in clinical remission (defined as PCDAI ≤10).

The proportions of subjects in clinical remission (defined as PCDAI ≤10) and clinical response (defined as reduction in PCDAI of at least 15 points from baseline) were assessed at Weeks 26 and 52.

At both Weeks 26 and 52, the proportion of subjects in clinical remission and clinical response was numerically higher in the high dose group compared to the low dose group (Table 14). The recommended maintenance regimen is 20 mg every other week for subjects weighing <40 kg and 40 mg every other week for subjects weighing ≥40 kg. Every week dosing is not the recommended maintenance dosing regimen [see Dosage and Administration (2.4)].

Table 14. Clinical Remission and Clinical Response in Study PCD-I
 | Low Maintenance Dose [The low maintenance dose was 20 mg every other week for subjects weighing ≥40 kg and 10 mg every other week for subjects weighing <40 kg.] (20 or 10 mg Every Other Week) N=95 | High Maintenance Dose [The high maintenance dose was 40 mg every other week for subjects weighing ≥ 40 kg and 20 mg every other week for subjects weighing <40 kg.] (40 or 20 mg Every Other Week) N=93
Week 26
Clinical Remission [Clinical remission defined as PCDAI ≤10.] | 28% | 39%
Clinical Response [Clinical response defined as reduction in PCDAI of at least 15 points from baseline.] | 48% | 59%
Week 52
Clinical Remission | 23% | 33%
Clinical Response | 28% | 42%

14.7 Clinical Studies in Adults with Ulcerative Colitis

The safety and efficacy of adalimumab were assessed in adult subjects with moderately to severely active ulcerative colitis (Mayo score 6 to 12 on a 12 point scale, with an endoscopy subscore of 2 to 3 on a scale of 0 to 3) despite concurrent or prior treatment with immunosuppressants such as corticosteroids, azathioprine, or 6‑MP in two randomized, double‑blind, placebo‑controlled clinical studies (Studies UC‑I and UC‑II). Both studies enrolled TNF‑blocker naïve subjects, but Study UC‑II also allowed entry of subjects who lost response to or were intolerant to TNF‑blockers. Forty percent (40%) of subjects enrolled in Study UC‑II had previously used another TNF‑blocker.

Concomitant stable doses of aminosalicylates and immunosuppressants were permitted. In Studies UC‑I and II, subjects were receiving aminosalicylates (69%), corticosteroids (59%) and/or azathioprine or 6‑MP (37%) at baseline. In both studies, 92% of subjects received at least one of these medications.

Induction of clinical remission (defined as Mayo score ≤2 with no individual subscores >1) at Week 8 was evaluated in both studies. Clinical remission at Week 52 and sustained clinical remission (defined as clinical remission at both Weeks 8 and 52) were evaluated in Study UC-II.

In Study UC‑I, 390 TNF‑blocker naïve subjects were randomized to one of three treatment groups for the primary efficacy analysis. The placebo group received placebo at Weeks 0, 2, 4 and 6. The 160/80 group received 160 mg adalimumab at Week 0 and 80 mg at Week 2, and the 80/40 group received 80 mg adalimumab at Week 0 and 40 mg at Week 2. After Week 2, subjects in both adalimumab treatment groups received 40 mg every other week.

In Study UC‑II, 518 subjects were randomized to receive either adalimumab 160 mg at Week 0, 80 mg at Week 2, and 40 mg every other week starting at Week 4 through Week 50, or placebo starting at Week 0 and every other week through Week 50. Corticosteroid taper was permitted starting at Week 8.

In both Studies UC‑I and UC‑II, a greater percentage of the subjects treated with 160/80 mg of adalimumab compared to subjects treated with placebo achieved induction of clinical remission. In Study UC‑II, a greater percentage of the subjects treated with 160/80 mg of adalimumab compared to subjects treated with placebo achieved sustained clinical remission (clinical remission at both Weeks 8 and 52) (Table 15).

Table 15. Induction of Clinical Remission in Studies UC-I and UC-II and Sustained Clinical Remission in Study UC-II (Percent of Subjects)
 | Study UC-I |  |  | Study UC-II
 | Placebo N=130 | Adalimumab 160/80 mg N=130 | Treatment Difference (95% CI) | Placebo N=246 | Adalimumab 160/80 mg N=248 | Treatment Difference (95% CI)
Induction of Clinical Remission (Clinical Remission at Week 8) | 9.2% | 18.5% | 9.3% [p<0.05 for adalimumab vs. placebo pairwise comparison of proportions.] (0.9%, 17.6%) | 9.3% | 16.5% | 7.2% (1.2%, 12.9%)
Sustained Clinical Remission (Clinical Remission at both Weeks 8 and 52) | N/A | N/A | N/A | 4.1% | 8.5% | 4.4% (0.1%, 8.6%)
Clinical remission is defined as Mayo score ≤2 with no individual subscores >1. CI=Confidence interval.

In Study UC-I, there was no statistically significant difference in clinical remission observed between the adalimumab 80/40 mg group and the placebo group at Week 8.

In Study UC-II, 17.3% (43/248) in the adalimumab group were in clinical remission at Week 52 compared to 8.5% (21/246) in the placebo group (treatment difference: 8.8%; 95% confidence interval (CI): [2.8%, 14.5%]; p<0.05).

In the subgroup of subjects in Study UC‑II with prior TNF‑blocker use, the treatment difference for induction of clinical remission appeared to be lower than that seen in the whole study population, and the treatment differences for sustained clinical remission and clinical remission at Week 52 appeared to be similar to those seen in the whole study population. The subgroup of subjects with prior TNF‑blocker use achieved induction of clinical remission at 9% (9/98) in the adalimumab group versus 7% (7/101) in the placebo group, and sustained clinical remission at 5% (5/98) in the adalimumab group versus 1% (1/101) in the placebo group. In the subgroup of subjects with prior TNF-blocker use, 10% (10/98) were in clinical remission at Week 52 in the adalimumab group versus 3% (3/101) in the placebo group.

14.8 Clinical Studies in Plaque Psoriasis

The safety and efficacy of adalimumab were assessed in randomized, double-blind, placebo-controlled studies in 1696 adult subjects with moderate to severe chronic plaque psoriasis (Ps) who were candidates for systemic therapy or phototherapy.

Study Ps-I evaluated 1212 subjects with chronic Ps with ≥10% body surface area (BSA) involvement, Physician's Global Assessment (PGA) of at least moderate disease severity, and Psoriasis Area and Severity Index (PASI) ≥12 within three treatment periods. In period A, subjects received placebo or adalimumab at an initial dose of 80 mg at Week 0 followed by a dose of 40 mg every other week starting at Week 1. After 16 weeks of therapy, subjects who achieved at least a PASI 75 response at Week 16, defined as a PASI score improvement of at least 75% relative to baseline, entered period B and received open-label 40 mg adalimumab every other week. After 17 weeks of open-label therapy, subjects who maintained at least a PASI 75 response at Week 33 and were originally randomized to active therapy in period A were re-randomized in period C to receive 40 mg adalimumab every other week or placebo for an additional 19 weeks. Across all treatment groups the mean baseline PASI score was 19 and the baseline Physician's Global Assessment score ranged from "moderate" (53%) to "severe" (41%) to "very severe" (6%).

Study Ps-II evaluated 99 subjects randomized to adalimumab and 48 subjects randomized to placebo with chronic plaque psoriasis with ≥10% BSA involvement and PASI ≥12. Subjects received placebo, or an initial dose of 80 mg adalimumab at Week 0 followed by 40 mg every other week starting at Week 1 for 16 weeks. Across all treatment groups the mean baseline PASI score was 21 and the baseline PGA score ranged from "moderate" (41%) to "severe" (51%) to "very severe" (8%).

Studies Ps-I and II evaluated the proportion of subjects who achieved "clear" or "minimal" disease on the 6-point PGA scale and the proportion of subjects who achieved a reduction in PASI score of at least 75% (PASI 75) from baseline at Week 16 (see Tables 16 and 17).

Additionally, Study Ps-I evaluated the proportion of subjects who maintained a PGA of "clear" or "minimal" disease or a PASI 75 response after Week 33 and on or before Week 52.

Table 16. Efficacy Results at 16 Weeks in Study Ps-I Number of Subjects (%)
 | Adalimumab 40 mg Every Other Week N=814 | Placebo N=398
PGA: Clear or minimal [Clear=no plaque elevation, no scale, plus or minus hyperpigmentation or diffuse pink or red coloration. Minimal=possible but difficult to ascertain whether there is slight elevation of plaque above normal skin, plus or minus surface dryness with some white coloration, plus or minus up to red coloration.] | 506 (62%) | 17 (4%)
PASI 75 | 578 (71%) | 26 (7%)

Table 17. Efficacy Results at 16 Weeks in Study Ps-II Number of Subjects (%)
 | Adalimumab 40 mg Every Other Week N=99 | Placebo N=48
PGA: Clear or minimal [Clear=no plaque elevation, no scale, plus or minus hyperpigmentation or diffuse pink or red coloration. Minimal=possible but difficult to ascertain whether there is slight elevation of plaque above normal skin, plus or minus surface dryness with some white coloration, plus or minus up to red coloration.] | 70 (71%) | 5 (10%)
PASI 75 | 77 (78%) | 9 (19%)

Additionally, in Study Ps-I, subjects on adalimumab who maintained a PASI 75 were re-randomized to adalimumab (N=250) or placebo (N=240) at Week 33. After 52 weeks of treatment with adalimumab, more subjects on adalimumab maintained efficacy when compared to subjects who were re-randomized to placebo based on maintenance of PGA of "clear" or "minimal" disease (68% vs. 28%) or a PASI 75 (79% vs. 43%).

A total of 347 stable responders participated in a withdrawal and retreatment evaluation in an open-label extension study. Median time to relapse (decline to PGA "moderate" or worse) was approximately 5 months. During the withdrawal period, no subject experienced transformation to either pustular or erythrodermic psoriasis. A total of 178 subjects who relapsed re-initiated treatment with 80 mg of adalimumab, then 40 mg every other week beginning at Week 1. At Week 16, 69% (123/178) of subjects had a response of PGA "clear" or "minimal".

A randomized, double-blind study (Study Ps-III) compared the efficacy and safety of adalimumab versus placebo in 217 adult subjects. Subjects in the study had to have chronic plaque psoriasis of at least moderate severity on the PGA scale, fingernail involvement of at least moderate severity on a 5-point Physician's Global Assessment of Fingernail Psoriasis (PGA-F) scale, a Modified Nail Psoriasis Severity Index (mNAPSI) score for the target-fingernail of ≥8, and either a BSA involvement of at least 10% or a BSA involvement of at least 5% with a total mNAPSI score for all fingernails of ≥20. Subjects received an initial dose of 80 mg adalimumab followed by 40 mg every other week (starting one week after the initial dose) or placebo for 26 weeks followed by open-label adalimumab treatment for an additional 26 weeks. This study evaluated the proportion of subjects who achieved "clear" or "minimal" assessment with at least a 2-grade improvement on the PGA-F scale and the proportion of subjects who achieved at least a 75% improvement from baseline in the mNAPSI score (mNAPSI 75) at Week 26.

At Week 26, a higher proportion of subjects in the adalimumab group than in the placebo group achieved the PGA-F endpoint. Furthermore, a higher proportion of subjects in the adalimumab group than in the placebo group achieved mNAPSI 75 at Week 26 (see Table 18).

Table 18. Efficacy Results at 26 Weeks
Endpoint | Adalimumab 40 mg Every Other Week [Subjects received 80 mg of adalimumab at Week 0, followed by 40 mg every other week starting at Week 1.] N=109 | Placebo N=108
PGA-F: ≥2-grade improvement and clear or minimal | 49% | 7%
mNAPSI 75 | 47% | 3%

Nail pain was also evaluated and improvement in nail pain was observed in Study Ps-III.

14.9 Clinical Studies in Hidradenitis Suppurativa

Two randomized, double-blind, placebo-controlled studies (Studies HS-I and II) evaluated the safety and efficacy of adalimumab in a total of 633 adult subjects with moderate to severe hidradenitis suppurativa (HS) with Hurley Stage II or III disease and with at least 3 abscesses or inflammatory nodules. In both studies, subjects received placebo or adalimumab at an initial dose of 160 mg at Week 0, 80 mg at Week 2, and 40 mg every week starting at Week 4 and continued through Week 11. Subjects used topical antiseptic wash daily. Concomitant oral antibiotic use was allowed in Study HS-II.

Both studies evaluated Hidradenitis Suppurativa Clinical Response (HiSCR) at Week 12. HiSCR was defined as at least a 50% reduction in total abscess and inflammatory nodule count with no increase in abscess count and no increase in draining fistula count relative to baseline (see Table 19). Reduction in HS-related skin pain was assessed using a Numeric Rating Scale in subjects who entered the study with an initial baseline score of 3 or greater on a 11 point scale.

In both studies, a higher proportion of adalimumab- than placebo-treated subjects achieved HiSCR (see Table 19).

Table 19. Efficacy Results at 12 Weeks in Subjects with Moderate to Severe Hidradenitis Suppurativa
 | HS Study I |  | HS Study II [19.3% of subjects in Study HS-II continued baseline oral antibiotic therapy during the study.]
 | Placebo | Adalimumab 40 mg Weekly | Placebo | Adalimumab 40 mg Weekly
Hidradenitis Suppurativa Clinical Response (HiSCR) | N=154; 40 (26%) | N=153; 64 (42%) | N=163; 45 (28%) | N=163; 96 (59%)

In both studies, from Week 12 to Week 35 (Period B), subjects who had received adalimumab were re-randomized to 1 of 3 treatment groups (adalimumab 40 mg every week, adalimumab 40 mg every other week, or placebo). Subjects who had been randomized to placebo were assigned to receive adalimumab 40 mg every week (Study HS-I) or placebo (Study HS-II).

During Period B, flare of HS, defined as ≥25% increase from baseline in abscesses and inflammatory nodule counts and with a minimum of 2 additional lesions, was documented in 22 (22%) of the 100 subjects who were withdrawn from adalimumab treatment following the primary efficacy timepoint in two studies.

14.10 Clinical Studies in Adults with Uveitis

The safety and efficacy of adalimumab were assessed in adult subjects with non-infectious intermediate, posterior and panuveitis excluding subjects with isolated anterior uveitis, in two randomized, double-masked, placebo-controlled studies (UV I and II). Subjects received placebo or adalimumab at an initial dose of 80 mg followed by 40 mg every other week starting one week after the initial dose. The primary efficacy endpoint in both studies was ´time to treatment failure´.

Treatment failure was a multi-component outcome defined as the development of new inflammatory chorioretinal and/or inflammatory retinal vascular lesions, an increase in anterior chamber (AC) cell grade or vitreous haze (VH) grade or a decrease in best corrected visual acuity (BCVA).

Study UV I evaluated 217 subjects with active uveitis while being treated with corticosteroids (oral prednisone at a dose of 10 to 60 mg/day). All subjects received a standardized dose of prednisone 60 mg/day at study entry followed by a mandatory taper schedule, with complete corticosteroid discontinuation by Week 15.

Study UV II evaluated 226 subjects with inactive uveitis while being treated with corticosteroids (oral prednisone 10 to 35 mg/day) at baseline to control their disease. Subjects subsequently underwent a mandatory taper schedule, with complete corticosteroid discontinuation by Week 19.

Clinical Response

Results from both studies demonstrated statistically significant reduction of the risk of treatment failure in subjects treated with adalimumab versus subjects receiving placebo. In both studies, all components of the primary endpoint contributed cumulatively to the overall difference between adalimumab and placebo groups (Table 20).

Table 20. Time to Treatment Failure in Studies UV I and UV II
 | UV I |  |  | UV II
 | Placebo; (N=107) | Adalimumab; (N=110) | HR; [95% CI] [HR of adalimumab versus placebo from proportional hazards regression with treatment as factor.] | Placebo; (N=111) | Adalimumab; (N=115) | HR; [95% CI]
Failure [Treatment failure at or after Week 6 in Study UV I, or at or after Week 2 in Study UV II, was counted as event. Subjects who discontinued the study were censored at the time of dropping out.] n (%) | 84 (78.5) | 60 (54.5) | 0.50; [0.36, 0.70] | 61 (55.0) | 45 (39.1) | 0.57; [0.39, 0.84]
Median Time to Failure (Months) [95% CI] | 3.0; [2.7, 3.7] | 5.6; [3.9, 9.2] | N/A | 8.3; [4.8, 12.0] | NE [NE=not estimable. Fewer than half of at-risk subjects had an event.] | N/A

Figure 3. Kaplan-Meier Curves Summarizing Time to Treatment Failure on or after Week 6 (Study UV I) or Week 2 (Study UV II)

Study UV I

Study UV II

Note: P#=Placebo (Number of Events/Number at Risk); A#=Adalimumab (Number of Events/Number at Risk).

15 REFERENCES

1. National Cancer Institute. Surveillance, Epidemiology, and End Results Database (SEER) Program. SEER Incidence Crude Rates, 17 Registries, 2000–2007.

16 HOW SUPPLIED/STORAGE AND HANDLING

ABRILADA™ (adalimumab-afzb) is supplied as a preservative-free, sterile, clear and colorless to very light brown solution for subcutaneous administration. The ABRILADA prefilled syringe and prefilled pen are not made with natural rubber latex. The following packaging configurations are available.

- ABRILADA Pen Carton - 40 mg/0.8 mL (One Count)
  ABRILADA (adalimumab-afzb) injection is supplied in a carton containing two alcohol preps and a single-dose pen. The single-dose pen contains a 1 mL prefilled glass syringe with a fixed thin wall, ½ inch needle, providing 40 mg/0.8 mL of ABRILADA.
  The NDC numbers are 0069-0325-01 and 0025-0325-01.
- ABRILADA Pen Carton - 40 mg/0.8 mL (Two Counts)
  ABRILADA (adalimumab-afzb) injection is supplied in a carton containing two alcohol preps and two single-dose pens. Each single-dose pen contains a 1 mL prefilled glass syringe with a fixed thin wall, ½ inch needle, providing 40 mg/0.8 mL of ABRILADA.
  The NDC numbers are 0069-0325-02 and 0025-0325-02.
- Prefilled Syringe Carton - 40 mg/0.8 mL (One Count)
  ABRILADA is supplied in a carton containing two alcohol preps and one dose tray. The dose tray consists of a single-dose, 1 mL prefilled glass syringe with a fixed thin wall, ½ inch needle, providing 40 mg/0.8 mL of ABRILADA.
  The NDC numbers are 0069-0328-01 and 0025-0328-01.
- Prefilled Syringe Carton - 40 mg/0.8 mL (Two Counts)
  ABRILADA is supplied in a carton containing two alcohol preps and two dose trays. Each dose tray consists of a single-dose, 1 mL prefilled glass syringe with a fixed thin wall, ½ inch needle, providing 40 mg/0.8 mL of ABRILADA.
  The NDC numbers are 0069-0328-02 and 0025-0328-02.
- Prefilled Syringe Carton - 20 mg/0.4 mL (Two Counts)
  ABRILADA is supplied in a carton containing two alcohol preps and two dose trays. Each dose tray consists of a single-dose, 1 mL prefilled glass syringe with a fixed thin wall, ½ inch needle, providing 20 mg/0.4 mL of ABRILADA.
  The NDC numbers are 0069-0333-02 and 0025-0333-02.
- Prefilled Syringe Carton - 10 mg/0.2 mL (Two Counts)
  ABRILADA is supplied in a carton containing two alcohol preps and two dose trays. Each dose tray consists of a single-dose, 1 mL prefilled glass syringe with a fixed thin wall, ½ inch needle, providing 10 mg/0.2 mL of ABRILADA.
  The NDC numbers are 0069-0347-02 and 0025-0347-02.
- Single-Dose Institutional Use Vial Carton - 40 mg/0.8 mL
  ABRILADA is supplied for institutional use only in a carton containing a single-dose, glass vial, providing 40 mg/0.8 mL of ABRILADA. The vial stopper is not made with natural rubber latex.
  The NDC numbers are 0069-0319-01 and 0025-0319-01.

Storage and Stability

Do not use beyond the expiration date on the container. ABRILADA must be refrigerated at 36°F to 46°F (2°C to 8°C). DO NOT FREEZE. Do not use if frozen even if it has been thawed.

Store in original carton until time of administration to protect from light.

If needed, for example when traveling, ABRILADA may be stored at room temperature up to a maximum of 86°F (30°C) for a period of up to 30 days, with protection from light. ABRILADA should be discarded if not used within the 30-day period. Record the date when ABRILADA is first removed from the refrigerator in the spaces provided on the ABRILADA pen carton or the prefilled syringe carton.

Do not store ABRILADA in extreme heat or cold.

17 PATIENT COUNSELING INFORMATION

Advise the patient or caregiver to read the FDA-approved patient labeling (Medication Guide and Instructions for Use).

Infections
Inform patients that ABRILADA may lower the ability of their immune system to fight infections. Instruct patients of the importance of contacting their healthcare provider if they develop any symptoms of infection, including tuberculosis, invasive fungal infections, and reactivation of hepatitis B virus infections [see Warnings and Precautions (5.1, 5.2, 5.4)].

Malignancies
Counsel patients about the risk of malignancies while receiving ABRILADA [see Warnings and Precautions (5.2)].

Hypersensitivity Reactions
Advise patients to seek immediate medical attention if they experience any symptoms of severe hypersensitivity reactions [see Warnings and Precautions (5.3)].

Other Medical Conditions
Advise patients to report any signs of new or worsening medical conditions such as congestive heart failure, neurological disease, autoimmune disorders, or cytopenias. Advise patients to report any symptoms suggestive of a cytopenia such as bruising, bleeding, or persistent fever [see Warnings and Precautions (5.5, 5.6, 5.8, 5.9)].

Instructions on Injection Technique

Inform patients that the first injection is to be performed under the supervision of a qualified healthcare professional. If a patient or caregiver is to administer ABRILADA, instruct them in injection techniques and assess their ability to inject subcutaneously to ensure the proper administration of ABRILADA [see Instructions for Use].

For patients who will use ABRILADA pen, tell them that they:

- Will only be able to press down the injection button when they are pushing the pen down firmly enough at the injection site.
- Will hear a click when the injection button is pressed all the way down. The click means the start of the injection.
- Will know the injection has finished and have received a full dose of medicine when they see the orange bar in the window, 5 seconds after hearing the 2nd click.

Instruct patients to dispose of their used needles and syringes or used pen in a FDA-cleared sharps disposal container immediately after use. Instruct patients not to dispose of loose needles and syringes or pen in their household trash. Instruct patients that if they do not have a FDA-cleared sharps disposal container, they may use a household container that is made of a heavy-duty plastic, can be closed with a tight-fitting and puncture-resistant lid without sharps being able to come out, upright and stable during use, leak-resistant, and properly labeled to warn of hazardous waste inside the container.

Instruct patients that when their sharps disposal container is almost full, they will need to follow their community guidelines for the correct way to dispose of their sharps disposal container. Instruct patients that there may be state or local laws regarding disposal of used needles and syringes. Refer patients to the FDA's website at http://www.fda.gov/safesharpsdisposal for more information about safe sharps disposal, and for specific information about sharps disposal in the state that they live in.

Instruct patients not to dispose of their used sharps disposal container in their household trash unless their community guidelines permit this. Instruct patients not to recycle their used sharps disposal container.

This product's labeling may have been updated. For the most recent prescribing information, please visit www.pfizer.com.

Manufactured by Pfizer Inc.
New York, NY 10001

Distributed by Pfizer Labs
Division of Pfizer Inc.
New York, NY 10001

US License No. 2001

LAB-1350-9.0

MEDICATION GUIDE
ABRILADA™ (AH brill-ah-dah)
(adalimumab-afzb)
injection, for subcutaneous use

Read the Medication Guide that comes with ABRILADA before you start taking it and each time you get a refill. There may be new information. This Medication Guide does not take the place of talking with your healthcare provider about your medical condition or treatment.

What is the most important information I should know about ABRILADA?
ABRILADA is a medicine that affects your immune system. ABRILADA can lower the ability of your immune system to fight infections. Serious infections have happened in people taking adalimumab products. These serious infections include tuberculosis (TB) and infections caused by viruses, fungi or bacteria that have spread throughout the body. Some people have died from these infections.

- Your healthcare provider should test you for TB before starting ABRILADA.
- Your healthcare provider should check you closely for signs and symptoms of TB during treatment with ABRILADA.

You should not start taking ABRILADA if you have any kind of infection unless your healthcare provider says it is okay.
Before starting ABRILADA, tell your healthcare provider if you:

- think you have an infection or have symptoms of infection such as:

- fever, sweats, or chills
- muscle aches
- cough
- shortness of breath
- blood in phlegm

- warm, red, or painful skin or sores on your body
- diarrhea or stomach pain
- burning when you urinate or urinate more often than normal
- feel very tired
- weight loss

- are being treated for an infection.
- get a lot of infections or have infections that keep coming back.
- have diabetes.
- have TB, or have been in close contact with someone with TB.
- were born in, lived in, or traveled to countries where there is more risk for getting TB. Ask your healthcare provider if you are not sure.
- live or have lived in certain parts of the country (such as the Ohio and Mississippi River valleys) where there is an increased risk for getting certain kinds of fungal infections (histoplasmosis, coccidioidomycosis, or blastomycosis). These infections may happen or become more severe if you use ABRILADA. Ask your healthcare provider if you do not know if you have lived in an area where these infections are common.
- have or have had hepatitis B.
- use the medicine ORENCIA (abatacept), KINERET (anakinra), RITUXAN (rituximab), IMURAN (azathioprine), or PURINETHOL (6–mercaptopurine, 6-MP).
- are scheduled to have major surgery

After starting ABRILADA, call your healthcare provider right away if you have an infection, or any sign of an infection.
ABRILADA can make you more likely to get infections or make any infection that you may have worse.
Cancer

- For children and adults taking tumor necrosis factor (TNF) blockers, including ABRILADA, the chances of getting cancer may increase.
- There have been cases of unusual cancers in children, teenagers, and young adults using TNF blockers.
- People with rheumatoid arthritis (RA), especially more serious RA, may have a higher chance for getting a kind of cancer called lymphoma.
- If you use TNF blockers including ABRILADA your chance of getting two types of skin cancer may increase (basal cell cancer and squamous cell cancer of the skin). These types of cancer are generally not life-threatening if treated. Tell your healthcare provider if you have a bump or open sore that does not heal.
- Some people receiving TNF blockers including ABRILADA developed a rare type of cancer called hepatosplenic T-cell lymphoma. This type of cancer often results in death. Most of these people were male teenagers or young men. Also, most people were being treated for Crohn's disease or ulcerative colitis with another medicine called IMURAN (azathioprine) or PURINETHOL (6-mercaptopurine, 6-MP).

What is ABRILADA?
ABRILADA is a medicine called a tumor necrosis factor (TNF) blocker. ABRILADA is used:

- To reduce the signs and symptoms of:
  - moderate to severe RA in adults. ABRILADA can be used alone, with methotrexate, or with certain other medicines.
  - moderate to severe polyarticular juvenile idiopathic arthritis (JIA) in children 2 years and older. ABRILADA can be used alone or with methotrexate.
  - psoriatic arthritis (PsA) in adults. ABRILADA can be used alone or with certain other medicines.
  - ankylosing spondylitis (AS) in adults.
  - moderate to severe hidradenitis suppurativa (HS) in adults.
- To treat moderate to severe Crohn's disease (CD) in adults and children 6 years of age and older.
- To treat moderate to severe ulcerative colitis (UC) in adults. It is not known if adalimumab products are effective in people who stopped responding to or could not tolerate TNF-blocker medicines.
- To treat moderate to severe chronic (lasting a long time) plaque psoriasis (Ps) in adults who have the condition in many areas of their body and who may benefit from taking injections or pills (systemic therapy) or phototherapy (treatment using ultraviolet light alone or with pills).
- To treat non-infectious intermediate, posterior, and panuveitis in adults.

What should I tell my healthcare provider before taking ABRILADA?
ABRILADA may not be right for you. Before starting ABRILADA, tell your healthcare provider about all of your medical conditions, including if you:

- have an infection. See "What is the most important information I should know about ABRILADA?"
- have or have had cancer.
- have any numbness or tingling or have a disease that affects your nervous system such as multiple sclerosis or Guillain-Barré syndrome.
- have or had heart failure.
- have recently received or are scheduled to receive a vaccine. You may receive vaccines, except for live vaccines while using ABRILADA. Children should be brought up to date with all vaccines before starting ABRILADA.
- are allergic to ABRILADA or to any of its ingredients. The ABRILADA prefilled syringe and prefilled pen are not made with natural rubber latex. See the end of this Medication Guide for a list of ingredients in ABRILADA.
- are pregnant or plan to become pregnant, breastfeeding or plan to breastfeed. You and your healthcare provider should decide if you should take ABRILADA while you are pregnant or breastfeeding.
- have a baby and you were using ABRILADA during your pregnancy. Tell your baby's healthcare provider before your baby receives any vaccines.

Tell your healthcare provider about all the medicines you take, including prescription and over-the-counter medicines, vitamins, and herbal supplements.
Especially tell your healthcare provider if you use:

- ORENCIA (abatacept), KINERET (anakinra), REMICADE (infliximab), ENBREL (etanercept), CIMZIA (certolizumab pegol) or SIMPONI (golimumab), because you should not use ABRILADA while you are also using one of these medicines.
- RITUXAN (rituximab). Your healthcare provider may not want to give you ABRILADA if you have received RITUXAN (rituximab) recently.
- IMURAN (azathioprine) or PURINETHOL (6–mercaptopurine, 6-MP).

Keep a list of your medicines with you to show your healthcare provider and pharmacist each time you get a new medicine.

How should I take ABRILADA?

- ABRILADA is given by an injection under the skin. Your healthcare provider will tell you how often to take an injection of ABRILADA. This is based on your condition to be treated. Do not inject ABRILADA more often than you were prescribed.
- See the Instructions for Use inside the carton for complete instructions for the right way to prepare and inject ABRILADA.
- Make sure you have been shown how to inject ABRILADA before you do it yourself. You can call your healthcare provider or 1-800-438-1985 if you have any questions about giving yourself an injection. Someone you know can also help you with your injection after they have been shown how to prepare and inject ABRILADA.
- Do not try to inject ABRILADA yourself until you are shown the right way to give the injections and read and understand the Instructions for Use. If your healthcare provider decides that you or a caregiver may be able to give your injections of ABRILADA at home, you should receive training on the right way to prepare and inject ABRILADA.
- Do not miss any doses of ABRILADA unless your healthcare provider says it is okay. If you forget to take ABRILADA, inject a dose as soon as you remember. Then, take your next dose at your regular scheduled time. This will put you back on schedule. In case you are not sure when to inject ABRILADA, call your healthcare provider or pharmacist.
- If you take more ABRILADA than you were told to take, call your healthcare provider.

What are the possible side effects of ABRILADA?
ABRILADA can cause serious side effects, including:
See "What is the most important information I should know about ABRILADA?"

- Serious Infections.
  Your healthcare provider will examine you for TB and perform a test to see if you have TB. If your healthcare provider feels that you are at risk for TB, you may be treated with medicine for TB before you begin treatment with ABRILADA and during treatment with ABRILADA. Even if your TB test is negative your healthcare provider should carefully monitor you for TB infections while you are taking ABRILADA. People who had a negative TB skin test before receiving adalimumab products have developed active TB. Tell your healthcare provider if you have any of the following symptoms while taking or after taking ABRILADA:

- cough that does not go away
- low grade fever

- weight loss
- loss of body fat and muscle (wasting)

- Hepatitis B infection in people who carry the virus in their blood.
  If you are a carrier of the hepatitis B virus (a virus that affects the liver), the virus can become active while you use ABRILADA. Your healthcare provider should do blood tests before you start treatment, while you are using ABRILADA, and for several months after you stop treatment with ABRILADA. Tell your healthcare provider if you have any of the following symptoms of a possible hepatitis B infection:

- muscle aches
- feel very tired
- dark urine
- skin or eyes look yellow
- little or no appetite
- vomiting

- clay-colored bowel movements
- fever
- chills
- stomach discomfort
- skin rash

- Allergic reactions. Allergic reactions can happen in people who use ABRILADA. Call your healthcare provider or get medical help right away if you have any of these symptoms of a serious allergic reaction:

- hives
- trouble breathing

- swelling of your face, eyes, lips or mouth

- Nervous system problems. Signs and symptoms of a nervous system problem include: numbness or tingling, problems with your vision, weakness in your arms or legs, and dizziness.
- Blood problems. Your body may not make enough of the blood cells that help fight infections or help to stop bleeding. Symptoms include a fever that does not go away, bruising or bleeding very easily, or looking very pale.
- New heart failure or worsening of heart failure you already have. Call your healthcare provider right away if you get new worsening symptoms of heart failure while taking ABRILADA, including:

- shortness of breath
- sudden weight gain

- swelling of your ankles or feet

- Immune reactions including a lupus-like syndrome. Symptoms include chest discomfort or pain that does not go away, shortness of breath, joint pain, or a rash on your cheeks or arms that gets worse in the sun. Symptoms may improve when you stop ABRILADA.
- Liver problems. Liver problems can happen in people who use TNF-blocker medicines. These problems can lead to liver failure and death. Call your healthcare provider right away if you have any of these symptoms:

- feel very tired
- poor appetite or vomiting

- skin or eyes look yellow
- pain on the right side of your stomach (abdomen)

- Psoriasis. Some people using adalimumab products had new psoriasis or worsening of psoriasis they already had. Tell your healthcare provider if you develop red scaly patches or raised bumps that are filled with pus. Your healthcare provider may decide to stop your treatment with ABRILADA.

Call your healthcare provider or get medical care right away if you develop any of the above symptoms. Your treatment with ABRILADA may be stopped.
The most common side effects of ABRILADA include:

- injection site reactions: redness, rash, swelling, itching, or bruising. These symptoms usually will go away within a few days. Call your healthcare provider right away if you have pain, redness or swelling around the injection site that does not go away within a few days or gets worse.
- upper respiratory infections (including sinus infections).
- headaches.
- rash.

These are not all of the possible side effects with ABRILADA. Tell your healthcare provider if you have any side effect that bothers you or that does not go away. Ask your healthcare provider or pharmacist for more information.
Call your doctor for medical advice about side effects. You may report side effects to FDA at 1-800-FDA-1088.

How should I store ABRILADA?

- Store ABRILADA in the refrigerator at 36°F to 46°F (2°C to 8°C). Store ABRILADA in the original carton until use to protect it from light.
- Do not freeze ABRILADA. Do not use ABRILADA if frozen, even if it has been thawed.
- Refrigerated ABRILADA may be used until the expiration date printed on the ABRILADA carton, pen or prefilled syringe. Do not use ABRILADA after the expiration date.
- If needed, for example when you are traveling, you may also store ABRILADA at room temperature up to 86°F (30°C) for up to 30 days. Store ABRILADA in the original carton until use to protect it from light.
- Throw away ABRILADA if it has been kept at room temperature and not been used within 30 days.
- Record the date you first remove ABRILADA from the refrigerator in the spaces provided on the ABRILADA pen carton or the prefilled syringe carton.
- Do not store ABRILADA in extreme heat or cold.
- The medicine in ABRILADA should be clear and colorless to very light brown. Do not use a pen or prefilled syringe if the liquid is cloudy, discolored, or has flakes or particles in it.
- Do not drop or crush ABRILADA. The prefilled syringe is glass.

Keep ABRILADA, injection supplies, and all other medicines out of the reach of children.

General information about the safe and effective use of ABRILADA
Medicines are sometimes prescribed for purposes other than those listed in a Medication Guide. Do not use ABRILADA for a condition for which it was not prescribed. Do not give ABRILADA to other people, even if they have the same condition. It may harm them. This Medication Guide summarizes the most important information about ABRILADA. If you would like more information, talk with your healthcare provider. You can ask your pharmacist or healthcare provider for information about ABRILADA that is written for health professionals.

What are the ingredients in ABRILADA?

Active ingredient: adalimumab-afzb
ABRILADA pen 40 mg/0.8 mL, ABRILADA 40 mg/0.8 mL prefilled syringe, ABRILADA 20 mg/0.4 mL prefilled syringe, ABRILADA 10 mg/0.2 mL prefilled syringe, and ABRILADA 40 mg/0.8 mL institutional use vial:

Inactive ingredients: edetate disodium dihydrate, L-histidine, L-histidine hydrochloride monohydrate, L-methionine, polysorbate 80, sucrose, and Water for Injection.

Manufactured by Pfizer Inc.
New York, NY 10001
Distributed by Pfizer Labs
Division of Pfizer Inc.
New York, NY 10001
US License No. 2001
LAB-1351-6.0

For more information go to www.Pfizer.com.

This Medication Guide has been approved by the U.S. Food and Drug Administration. Revised: 4/2024

INSTRUCTIONS FOR USE

ABRILADA (AH brill-ah-dah)
(adalimumab-afzb)
40 mg/0.8 mL
Single-dose Prefilled Pen
Injection, for subcutaneous (under the skin) use

Keep this leaflet. These instructions show step by step directions on how to prepare and give an injection.

Storage Information:

- Store your ABRILADA pen in the refrigerator at 36°F to 46°F (2°C to 8°C).
- Store ABRILADA pen in the original carton until use to protect from light.
- Do not freeze ABRILADA. Do not use ABRILADA if frozen, even if it has been thawed.
- Refrigerated ABRILADA may be used until the expiration date printed on the ABRILADA carton or pen. Do not use ABRILADA after the expiration date.
- If needed, for example when you are traveling, you may also store ABRILADA at room temperature up to 86°F (30°C) for up to 30 days. Store ABRILADA in the original carton until use to protect it from light.
- Throw away ABRILADA if it has been kept at room temperature and not been used within 30 days.
- Record the date you first remove ABRILADA from the refrigerator in the spaces provided on the ABRILADA pen carton.
- Do not store ABRILADA in extreme heat or cold.
- Do not use the pen if the liquid is cloudy, discolored, or has flakes or particles in it.
  Note: The ABRILADA prefilled pen is not made with natural rubber latex.

Keep ABRILADA, injection supplies, and all other medicines out of the reach of children.

ABRILADA for injection comes in a disposable (throw away) single-use pen that contains a single dose of medicine.

ABRILADA for injection can be given by a patient, caregiver or healthcare provider. Do not try to inject ABRILADA yourself until you are shown the right way to give the injections and read and understand the Instructions for Use. If your healthcare provider decides that you or a caregiver may be able to give your injections of ABRILADA at home, you should receive training on the right way to prepare and inject ABRILADA. It is important that you read, understand, and follow these instructions so that you inject ABRILADA the right way.

It is important to talk to your healthcare provider to be sure you understand your ABRILADA dosing instructions. To help you remember when to inject ABRILADA, you can mark your calendar ahead of time. Call your healthcare provider if you or your caregiver have any questions about the right way to inject ABRILADA.

Step 1. Supplies you need

- You will need the following supplies for each injection of ABRILADA. Find a clean, flat surface to place the supplies on.
  - 1 ABRILADA pen (included inside the carton)
  - 1 alcohol swab (included inside the carton)
  - 1 cotton ball or gauze pad (not included in your ABRILADA carton)
  - 1 puncture resistant sharps disposal container for pen disposal (not included in your ABRILADA carton). See Step 10 "Dispose of used pen" at the end of this Instructions for Use.

Step 2. Getting ready

- Remove the ABRILADA carton from the refrigerator.
- Make sure the name ABRILADA appears on the carton and prefilled pen label.
- Take out 1 ABRILADA pen and the alcohol swab. Keep your pen out of direct sunlight. Put the original carton with any unused pens back in the refrigerator.
- Do not use your pen if:
  - your pen or the carton containing the pen has been dropped
  - it has been frozen or thawed
  - it has been kept in direct sunlight
  - it appears to be damaged
  - the seals on a new carton are broken
  - it has been out of the refrigerator for more than 30 days
  - the expiration date has passed
  - the liquid is cloudy, discolored or has flakes or particles
- For a more comfortable injection, you may leave your pen at room temperature for 15 to 30 minutes before your injection.
- Do not warm ABRILADA in any other way (for example, do not warm it in a microwave or in hot water).
- Do not shake your pen. Shaking can damage your medicine.
- Wash your hands with soap and water, and dry completely.
- Do not remove the cap until you are ready to inject.

- Look carefully at your medicine in the window.
- Make sure the medicine in the pen is clear and colorless to very light brown and free from flakes or particles.
- It is normal to see one or more air bubbles in the window.
- Check the expiration date on the pen label. The location of the expiration date on the pen label is shown below. Do not use the pen if the expiration date has passed.
  If you have any questions about your medicine, please contact your healthcare provider or pharmacist.

- Choose a different injection site each time you give an injection:
  - Only use the front of your thighs or your lower abdomen (belly) as shown. If you choose your abdomen, do not use the area 2 inches around your belly button (navel).
  - Each new injection should be given at least one inch from a site you used before.
- Do not inject into bony areas or areas on your skin that are bruised, red, sore (tender) or hard. Avoid injecting into areas with scars or stretch marks.
  - If you have psoriasis, do not inject directly into any raised, thick, red, or scaly skin patches or lesions on your skin.
- Do not inject through your clothes.
- Wipe the injection site with the alcohol swab.
- Allow the injection site to dry. Do not fan or blow on the clean area.
- Do not touch this area again before giving the injection.

- Twist and pull off the cap.
- Throw the cap away into a sharps disposal container. You will not need it again.
  Important: Handle your pen with care to avoid an accidental needle stick injury.
  Note: A needle cover stays inside the cap after cap removal.

- Push your pen firmly against the skin at 90 degrees, as shown in the diagram.
  Note: The needle goes into the skin as you push your pen down. You will only be able to press down the injection button in Step 7 when you are pushing down firmly enough.
- Keep your pen pushed against the skin until Step 9.

- Press the injection button all the way down and you will hear a click. The click means the start of the injection.
- Keep holding your pen firmly against the skin while the orange bar moves across the window. You will hear a 2nd click.
- Wait for at least 5 more seconds after the 2nd click to make sure you get the full dose of medicine.
  Note: If you cannot press down the injection button, it is because you are not pushing the pen down firmly enough at the injection site. See the Question and Answer section on the right side of this Instructions for Use for more information on what to do if the injection button does not press down.

- You should see an orange bar in the window.
- Do not remove your pen until you have waited at least 5 seconds after the 2nd click and until the orange bar completely fills the window.

- Remove your pen from the skin.
  Note: After you remove your pen from the skin, the needle will be automatically covered.
- If the window has not turned orange, this means you have not received a full dose. Call your healthcare provider or pharmacist right away.
- Do not inject another dose.

- Put your used pen in a FDA-cleared sharps disposal container right away after use. Do not throw away (dispose of) pens in your household trash.
- If you do not have a FDA-cleared sharps disposal container, you may use a household container that is:
  - made of heavy duty plastic,
  - can be closed with a tight-fitting, puncture-resistant lid, without sharps being able to come out,
  - upright and stable during use,
  - leak-resistant, and
  - is properly labeled to warn of hazardous waste inside the container.
- When your sharps disposal container is almost full, you will need to follow your community guidelines for the right way to dispose of your sharps disposal container. There may be state or local laws about how you should throw away used needles and syringes. For more information about safe sharps disposal, and for specific information about sharps disposal in the state that you live in, go to the FDA's website at http://www.fda.gov/safesharpsdisposal.
- Do not dispose of your used sharps disposal container in your household trash unless your community guidelines permit this. Do not recycle your used sharps disposal container.

- Look closely at your injection site. If there is blood, use a clean cotton ball or gauze pad to press lightly on the injection area for a few seconds.
- Do not rub the injection site.
  Note: Store any unused pens in the refrigerator in the original carton.

Questions and Answers

What should I do with my pen if it has been dropped?
Do not use it, even if it looks undamaged. Dispose of your pen in the same way as a used pen. You will need to use a new pen to give your injection.

Can I use my pen straight from the refrigerator?
Yes, however you may find that using the pen at room temperature reduces stinging or discomfort. If you allow your pen to reach room temperature before use, you must keep it away from direct sunlight as this can damage your medicine.

What should I do if I need to travel?
When you are traveling, you may store your pen in its carton at room temperature up to 86°F (30°C) for up to 30 days.

Is it okay to shake my pen before I use it?
No, do not shake your pen. Shaking can damage your medicine. When you check your medicine, gently tilt your pen back and forth while looking carefully into the window. It is normal to see one or more air bubbles.

Do I need to remove any air bubbles before using my pen?
No, do not attempt to remove air bubbles.

Drops of medicine have appeared at the needle tip. Is this okay?
Yes, it is normal to see a few drops of medicine at the needle tip when you remove the cap.

Can I re-insert the needle if I change my mind where I want to inject?
No, you should not re-insert the needle into your skin. If you change your mind, you will need a replacement pen if the needle has already been inserted into the skin. After the injection button has been pressed, you must not lift your pen from the skin until the injection has finished.

I pushed my pen against the skin but could not press the button down. What should I do?
Take your finger off the injection button and push your pen down more firmly against the skin. Then try pushing the button again. If this does not work, stretching the skin may make the injection site firmer, making pressing the injection button easier.

Can I pinch or stretch the skin at the injection area?
Yes, pinching or stretching the skin before injection may make the injection site firmer, making it easier to press the injection button.

Do I need to keep my finger pressed on the injection button for the whole injection?
No, you can stop pressing the button when the injection has started. However, make sure you keep holding the pen firmly against the skin. The pen will continue to deliver your medicine.

How long will the injection take?
From the time the dose begins until you hear the 2nd click, it usually takes 3 to 10 seconds. After the 2nd click, you should continue to hold your pen in place for at least 5 more seconds to make sure you give the full dose.

What should I do if I see more than a small drop of medicine on the skin after giving my injection?
Nothing this time, but for your next injection wait a little longer before removing the pen from the skin to make sure all of the medicine went into your skin.

What should I do if I have any questions about my ABRILADA pen or medicine?
Contact your healthcare provider or pharmacist.

This Instructions for Use has been approved by the U.S. Food and Drug Administration.

Manufactured by Pfizer Inc.
New York, NY 10001

Distributed by Pfizer Labs
Division of Pfizer Inc.
New York, NY 10001

US License No. 2001

LAB-1352-4.0

Revised: 4/2024

INSTRUCTIONS FOR USE

ABRILADA (AH brill-ah-dah)
(adalimumab-afzb)
10 mg/0.2 mL, 20 mg/0.4 mL, 40 mg/0.8 mL
Single-dose Prefilled Syringe

Injection, for subcutaneous (under the skin) use only

Keep this leaflet. These instructions show step by step directions on how to prepare and give an injection.

Storage Information:

- Store your ABRILADA prefilled syringe in the refrigerator at 36°F to 46°F (2°C to 8°C).
- Store ABRILADA prefilled syringe in the original carton until use to protect from light.
- Do not freeze ABRILADA. Do not use ABRILADA if frozen, even if it has been thawed.
- Refrigerated ABRILADA may be used until the expiration date printed on the ABRILADA carton or prefilled syringe. Do not use ABRILADA after the expiration date.
- If needed, for example when you are traveling, you may also store ABRILADA at room temperature up to 86°F (30°C) for up to 30 days. Store ABRILADA in the original carton until use to protect it from light.
- Throw away ABRILADA if it has been kept at room temperature and not been used within 30 days.
- Record the date you first remove ABRILADA from the refrigerator in the spaces provided on the ABRILADA prefilled syringe carton.
- Do not store ABRILADA in extreme heat or cold.
- Do not use a prefilled syringe if the liquid is cloudy, discolored, or has flakes or particles in it.
- Do not drop or crush ABRILADA. The prefilled syringe is glass.
  Note: The ABRILADA prefilled syringe is not made with natural rubber latex.

Keep ABRILADA, injection supplies, and all other medicines out of the reach of children.

ABRILADA for injection comes in a disposable (throw away) single use prefilled syringe that contains a single dose of medicine.

ABRILADA for injection can be given by a patient, caregiver or healthcare provider. Do not try to inject ABRILADA yourself until you are shown the right way to give the injections and read and understand the Instructions for Use. If your healthcare provider decides that you or a caregiver may be able to give your injections of ABRILADA at home, you should receive training on the right way to prepare and inject ABRILADA. It is important that you read, understand, and follow these instructions so that you inject ABRILADA the right way.

It is important to talk to your healthcare provider to be sure you understand your ABRILADA dosing instructions. To help you remember when to inject ABRILADA, you can mark your calendar ahead of time. Call your healthcare provider if you or your caregiver have any questions about the right way to inject ABRILADA.

Step 1. Supplies you need

- You will need the following supplies for each injection of ABRILADA. Find a clean, flat surface to place the supplies on.
  - 1 ABRILADA prefilled syringe in a tray inside the carton
  - 1 alcohol swab inside the carton
  - 1 cotton ball or gauze pad (not included in your ABRILADA carton)
  - 1 puncture resistant sharps disposal container for prefilled syringe disposal (not included in your ABRILADA carton). See Step 10 "Dispose of used syringe" at the end of this Instructions for Use.

Step 2. Getting ready

- Remove ABRILADA carton from the refrigerator.
- Open the carton and take out the tray containing your prefilled syringe.
- Make sure the name ABRILADA appears on the dose tray and prefilled syringe label.
- Check your carton and tray. Do not use if:
  - it has been dropped
  - it has been frozen or thawed
  - it appears to be damaged
  - the seals on a new carton are broken
  - it has been out of the refrigerator for more than 30 days
  - the expiration date has passed
Wash your hands with soap and water, and dry completely.
  If you have any questions about your medicine, please contact your healthcare provider or pharmacist.

- Peel back the paper seal on the tray.
- Remove 1 prefilled syringe from the tray and put the original carton with any unused prefilled syringes back in the refrigerator.
- Do not use your syringe if:
  - it appears to be damaged
  - It has been kept in direct sunlight
  - liquid is cloudy, discolored, or has flakes or particles
- Do not shake your syringe. Shaking can damage your medicine.
- For a more comfortable injection, leave the prefilled syringe at room temperature for 15 to 30 minutes before your injection.
- Do not warm ABRILADA in any other way (for example, do not warm it in a microwave or in hot water).
- Do not remove the needle cover from your prefilled syringe until you are ready to inject.
  Always hold the prefilled syringe by the barrel to prevent damage.

- Look carefully at your medicine in the window.
- Make sure the medicine in the prefilled syringe is clear and colorless to very light brown and free from flakes or particles.
- It is normal to see one or more air bubbles in the window.
- Check the expiration date on the prefilled syringe label as shown in the figure in Step 1. Do not use the prefilled syringe if the expiration date has passed.
  If you have any questions about your medicine, please contact your healthcare provider or pharmacist.

- Choose a different injection site each time you give an injection.
  - Only use the front of your thighs or your lower abdomen (belly) as shown. If you choose your abdomen, do not use the area 2 inches around your belly button (navel).
  - Each new injection should be given at least one inch from a site you used before.
- Do not inject into bony areas or areas on your skin that are bruised, red, sore (tender) or hard. Avoid injecting into areas with scars or stretch marks.
  - If you have psoriasis, do not inject directly into any raised, thick, red, or scaly skin patches or lesions on your skin.
- Do not inject through your clothes.
- Wipe the injection site with the alcohol swab.
- Allow the injection site to dry. Do not fan or blow on the clean area.
- Do not touch this area again before giving the injection.

- Hold the prefilled syringe by the barrel. Carefully pull the needle cover straight off and away from your body when you are ready to inject.
- It is normal to see a drop of liquid at the end of the needle.
- Throw the needle cover away into a sharps disposal container.
  Note: Be careful when you handle your prefilled syringe to avoid an accidental needle stick injury.

- Gently pinch up a fold of skin in the cleaned injection site area.
- Insert the needle to its full depth into the skin, at a 45 degree angle, as shown.
- After the needle is inserted, release the pinched skin.

- Using slow and constant pressure, push the plunger rod all the way down until the barrel is empty.
  Note: It is recommended to hold your prefilled syringe in the skin for an additional 5 seconds after the plunger has been pressed down completely to make sure you get the full dose of medicine.
- Pull the needle out of the skin at the same angle at which it entered.

- Check that your medicine has completely emptied from your prefilled syringe. If the gray stopper is not in the position shown, you may not have injected all of your medicine. Contact your healthcare provider right away.
- Never re-insert the needle.
- Never put the cap back on the needle.

- Put your used syringe in a FDA-cleared sharps disposal container right away after use. Do not throw away (dispose of) syringes in your household trash.
- If you do not have a FDA-cleared sharps disposal container, you may use a household container that is:
  - made of heavy duty plastic,
  - can be closed with a tight-fitting, puncture-resistant lid, without sharps being able to come out,
  - upright and stable during use,
  - leak-resistant, and
  - is properly labeled to warn of hazardous waste inside the container.
- When your sharps disposal container is almost full, you will need to follow your community guidelines for the right way to dispose of your sharps disposal container. There may be state or local laws about how you should throw away used needles and syringes. For more information about safe sharps disposal, and for specific information about sharps disposal in the state that you live in, go to the FDA's website at http://www.fda.gov/safesharpsdisposal.
- Do not dispose of your used sharps disposal container in your household trash unless your community guidelines permit this. Do not recycle your used sharps disposal container.

- Look closely at your injection site. If there is blood, use a clean cotton ball or gauze pad to press lightly on the injection area for a few seconds.
- Do not rub the site.
  Note: Store any unused syringes in the refrigerator in the original carton.

Questions and Answers

What should I do with my prefilled syringe if it has been dropped?
Do not use it if it has been dropped or the carton containing your prefilled syringe has been dropped even if it looks undamaged. Dispose of your prefilled syringe in the same way as a used prefilled syringe. You will need to use a new prefilled syringe to give your injection.

Can I use my prefilled syringe straight from the refrigerator?
Yes, however you may find that using the prefilled syringe at room temperature reduces stinging or discomfort. If you allow your prefilled syringe to reach room temperature before use, you must keep it away from direct sunlight as this can damage your medicine.

What should I do if I need to travel?
When you are traveling, you may store your prefilled syringe in its carton at room temperature up to 86°F (30°C) for up to 30 days.

Is it okay to shake my prefilled syringe before I use it?
No, do not shake your prefilled syringe. Shaking can damage your medicine. When you check your medicine, gently tilt your syringe back and forth while looking carefully into the window. It is normal to see one or more bubbles.

Do I need to remove any air bubbles before using my prefilled syringe?
No, do not attempt to remove air bubbles.

Drops of medicine have appeared at the needle tip. Is this okay?
Yes, it is normal to see a few drops of medicine at the needle tip when you remove the needle cover.

Can I re-insert the needle into my skin?
No, you should not re-insert the needle into the skin. You will need a replacement prefilled syringe if the needle has already been inserted into the skin.

How long will the injection take?
Dose delivery will take approximately 2 to 5 seconds. Remember to hold your prefilled syringe in place for at least 5 seconds after the plunger has been pushed down all the way.

What should I do if I have any questions about my prefilled syringe or medicine?
Contact your healthcare provider or pharmacist.

This Instructions for Use has been approved by the U.S. Food and Drug Administration.

Manufactured by Pfizer Inc.
New York, NY 10001

Distributed by Pfizer Labs
Division of Pfizer Inc.
New York, NY 10001

US License No. 2001

LAB-1353-4.0

Revised: 4/2024

PRINCIPAL DISPLAY PANEL - 0.8 mL Prefilled Pen Label - NDC 0069-0318-01

ALWAYS DISPENSE WITH MEDICATION GUIDE
NDC 0069-0318-01

Abrilada™
(adalimumab-afzb)
Injection
Citrate-free

Rx Only
Single-dose
prefilled pen

40 mg/0.8 mL

For Subcutaneous Injection Only

Dosage: See Prescribing Information.

Manufactured by Pfizer Inc.
New York, NY 10001
Distributed by Pfizer Labs
Division of Pfizer Inc.
New York, NY 10001
US License No. 2001

Store in refrigerator at 36°F to 46°F
(2°C to 8°C). DO NOT FREEZE.
Protect from light.

PRINCIPAL DISPLAY PANEL - Kit Carton - NDC 0069-0325-02

ALWAYS DISPENSE WITH MEDICATION GUIDE
NDC 0069-0325-02

Abrilada™
(adalimumab-afzb)
Injection

Two Single-Dose Prefilled Pens
For Subcutaneous Injection Only

This carton contains:

- 2 Prefilled Pens
- 2 Alcohol Preps
- 1 Prescribing Information
- 1 Instructions for Use
  with Medication Guide

Do not shake.

Keep out of reach of children

Citrate-free
Rx only

40 mg/0.8 mL

Two Single-Dose Prefilled Pens
29 Gauge Needle

▼ To Open

PRINCIPAL DISPLAY PANEL - 0.8 mL Syringe Label

Abrilada™
(adalimumab-afzb) Injection

NDC 0069-0317-01

For Subcutaneous Injection Only
Rx only

40 mg/0.8 mL

Single-Dose

Mfg. by Pfizer Inc.
NY, NY 10017

US License No. 2001

PRINCIPAL DISPLAY PANEL - 0.8 mL Syringe Tray Label

PEEL

PEEL

PEEL

NDC 0069-0317-01

Abrilada™
(adalimumab-afzb)
Injection

Citrate-free

40 mg/0.8 mL

One Single-Dose Prefilled Syringe
For Subcutaneous Injection Only
No preservative

Rx only

Pfizer

Manufactured by Pfizer Inc.
New York, NY 10017
US License No. 2001
Return to pharmacy if dose tray seal is broken or missing.

704180

Do not use beyond the expiration
date on the container.

Store in refrigerator at 36°F to 46°F
(2°C to 8°C).

DO NOT FREEZE. Do not use if frozen
even if it has been thawed.

Store in original carton until time of
administration to protect from light.

An ABRILADA prefilled syringe may be
stored at room temperature up to a
maximum of 86°F (30°C) for up to 30
days with protection from light.

Dosage: See Prescribing Information.

PRINCIPAL DISPLAY PANEL - Kit Carton - NDC 0069-0328-02

ALWAYS DISPENSE WITH MEDICATION GUIDE
NDC 0069-0328-02

Abrilada™
(adalimumab-afzb)
Injection

Two Single-Dose Prefilled Syringes
For Subcutaneous Injection Only

This carton contains:

- 2 Prefilled Syringes
- 2 Alcohol Preps
- 1 Instructions for Use
- 1 Medication Guide
- 1 Package Insert

Do not shake
Keep out of reach of children

Citrate-free
Rx only

40 mg/0.8 mL

Two Single-Dose Prefilled Syringes
29 Gauge Needle

▼ To Open

PRINCIPAL DISPLAY PANEL - 0.4 mL Syringe Label

Abrilada™
(adalimumab-afzb) Injection

NDC 0069-0329-01

For Subcutaneous Injection Only
Rx only

20 mg/0.4 mL

Single-Dose

Mfg. by Pfizer Inc.
NY, NY 10017

US License No. 2001

PRINCIPAL DISPLAY PANEL - 0.4 mL Syringe Tray Label

PEEL

PEEL

PEEL

NDC 0069-0329-01

Abrilada™
(adalimumab-afzb)
Injection

Citrate-free

20 mg/0.4 mL

One Single-Dose Prefilled Syringe
For Subcutaneous Injection Only
No preservative

Rx only

Pfizer

Manufactured by Pfizer Inc.
New York, NY 10017
US License No. 2001
Return to pharmacy if dose tray seal is broken or missing.

704187

Do not use beyond the expiration
date on the container.

Store in refrigerator at 36°F to 46°F
(2°C to 8°C).

DO NOT FREEZE. Do not use if frozen
even if it has been thawed.

Store in original carton until time of
administration to protect from light.

An ABRILADA prefilled syringe may be
stored at room temperature up to a
maximum of 86°F (30°C) for up to 30
days with protection from light.

Dosage: See Prescribing Information.

PRINCIPAL DISPLAY PANEL - Kit Carton - NDC 0069-0333-02

ALWAYS DISPENSE WITH MEDICATION GUIDE
NDC 0069-0333-02

Abrilada™
(adalimumab-afzb)
Injection

Two Single-Dose Prefilled Syringes
For Subcutaneous Injection Only

This carton contains:

- 2 Prefilled Syringes
- 2 Alcohol Preps
- 1 Instructions for Use
- 1 Medication Guide
- 1 Package Insert

Do not shake

Keep out of reach of children

Citrate-free
Rx only

20 mg/0.4 mL

Two Single-Dose Prefilled Syringes
29 Gauge Needle

▼ To Open

PRINCIPAL DISPLAY PANEL - 0.2 mL Syringe Label

Abrilada™
(adalimumab-afzb) Injection

NDC 0069-0331-01

For Subcutaneous Injection Only
Rx only

10 mg/0.2 mL

Single-Dose

Mfg. by Pfizer Inc
NY, NY 10017

US License No. 2001

PRINCIPAL DISPLAY PANEL - 0.2 mL Syringe Tray Label

PEEL

PEEL

PEEL

NDC 0069-0331-01

Abrilada™
(adalimumab-afzb)
Injection

Citrate-free

10 mg/0.2 mL

One Single-Dose Prefilled Syringe
For Subcutaneous Injection Only
No preservative

Rx only

Pfizer

Manufactured by Pfizer Inc
New York, NY 10017
US License No. 2001
Return to pharmacy if dose tray seal is broken or missing.

ABPFSLD69-1

Do not use beyond the expiration
date on the container.

Store in refrigerator at 36°F to 46°F
(2°C to 8°C).

DO NOT FREEZE. Do not use if frozen
even if it has been thawed.

Store in original carton until time of
administration to protect from light.

An ABRILADA prefilled syringe may be
stored at room temperature up to a
maximum of 86°F (30°C) for up to 30
days with protection from light.

Dosage: See Prescribing Information.

PRINCIPAL DISPLAY PANEL - Kit Carton - NDC 0069-0347-02

ALWAYS DISPENSE WITH MEDICATION GUIDE
NDC 0069-0347-02

Abrilada™
(adalimumab-afzb)
Injection

Two Single-Dose Prefilled Syringes
For Subcutaneous Injection Only

This carton contains:

- 2 Prefilled Syringes
- 2 Alcohol Preps
- 1 Instructions for Use
- 1 Medication Guide
- 1 Package Insert

Do not shake

Keep out of reach of children

Citrate-free
Rx only

10 mg/0.2 mL

Two Single-Dose Prefilled Syringes
29 Gauge Needle

▼ To Open

PRINCIPAL DISPLAY PANEL - 0.8 mL Vial Label

ALWAYS DISPENSE WITH MEDICATION GUIDE

NDC 0069-0319-01
One Single-Dose Vial

Abrilada™
(adalimumab-afzb)
Injection

40 mg/0.8 mL

For Subcutaneous
Injection Only

Rx only

PRINCIPAL DISPLAY PANEL - 0.8 mL Vial Carton

ALWAYS DISPENSE WITH
MEDICATION GUIDE

NDC 0069-0319-01

Citrate-free

Abrilada™
(adalimumab-afzb)
Injection

40 mg/0.8 mL

For Subcutaneous Injection Only

One Single-Dose Vial
Discard Unused Portion
For Institutional Use Only
Contains no preservatives
Do not shake

Keep out of reach of children.
Rx only

Pfizer